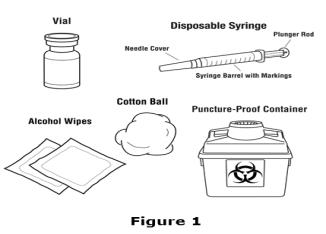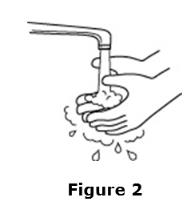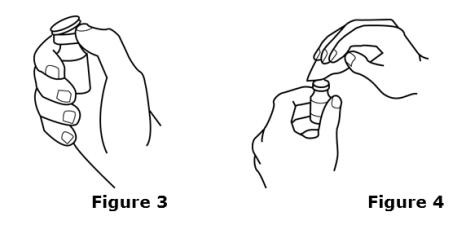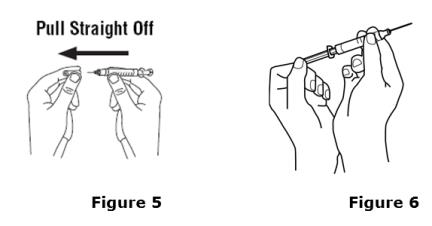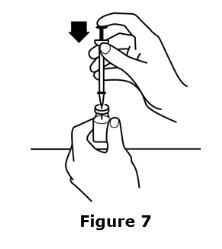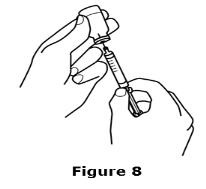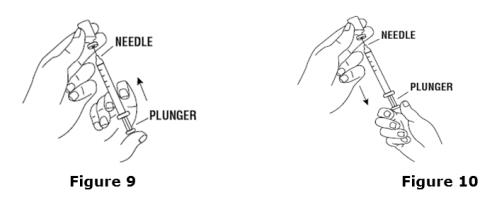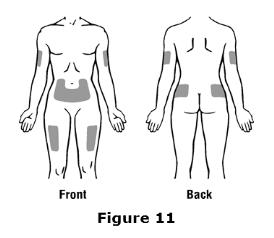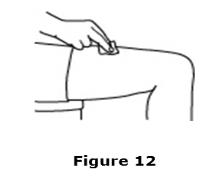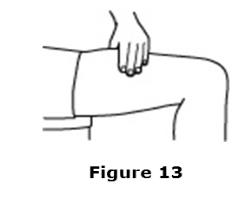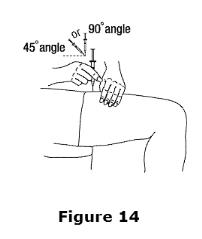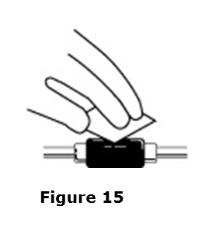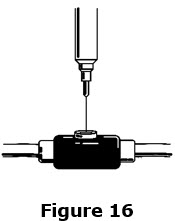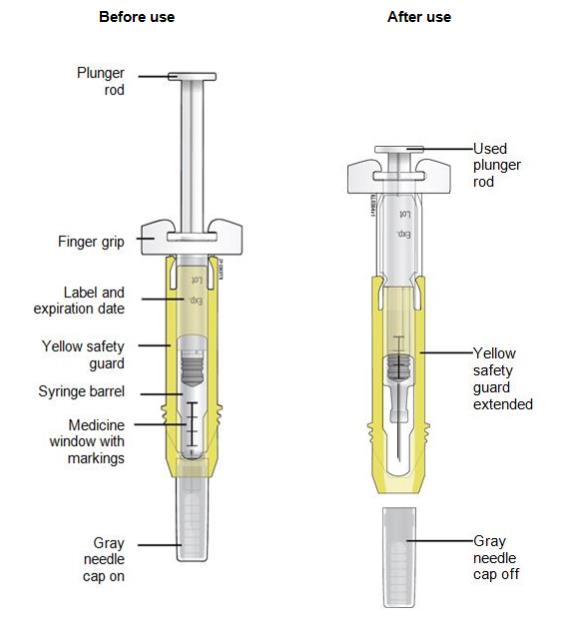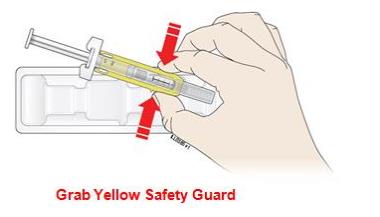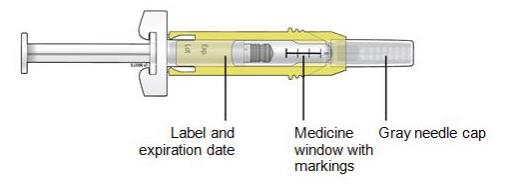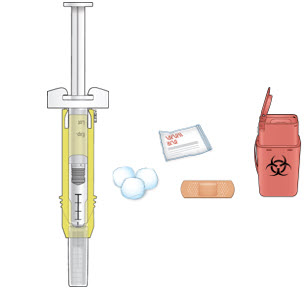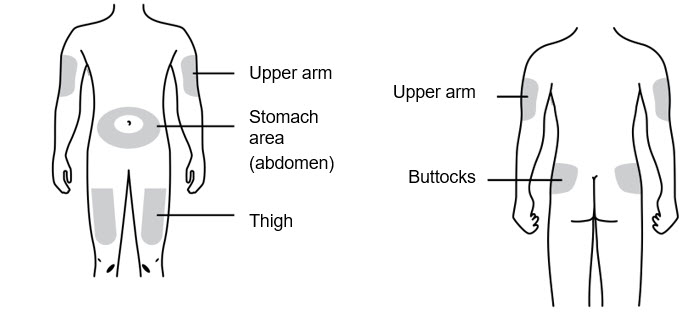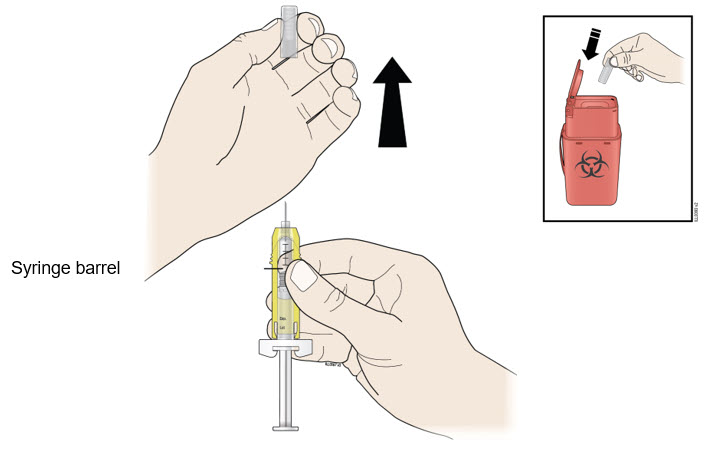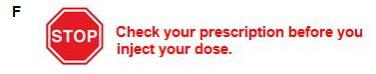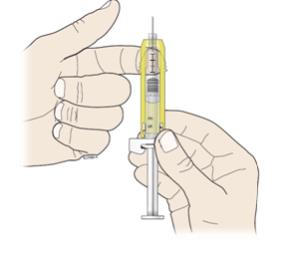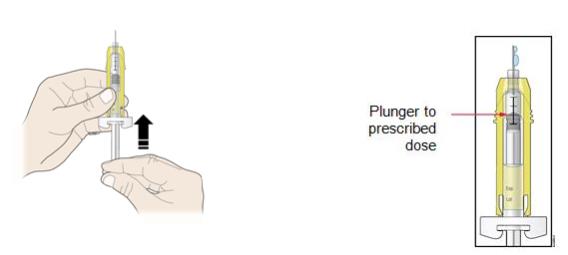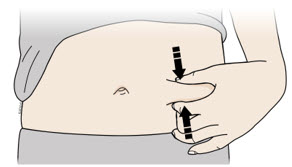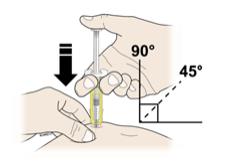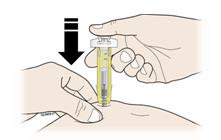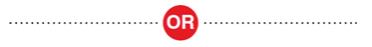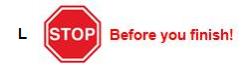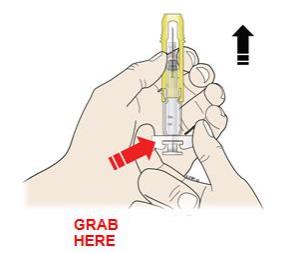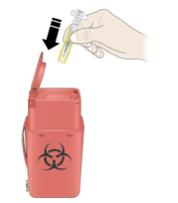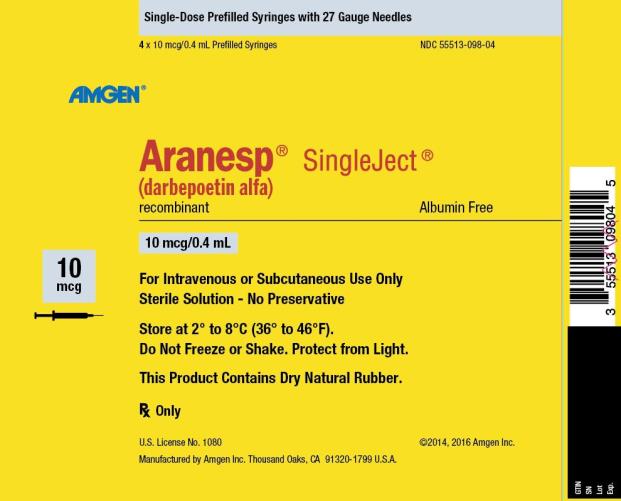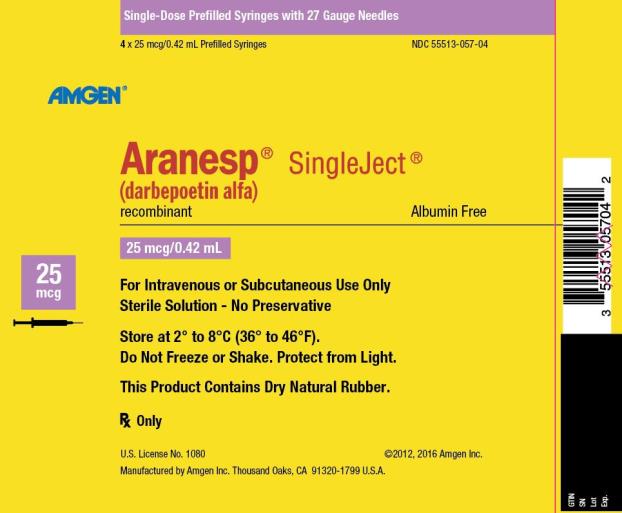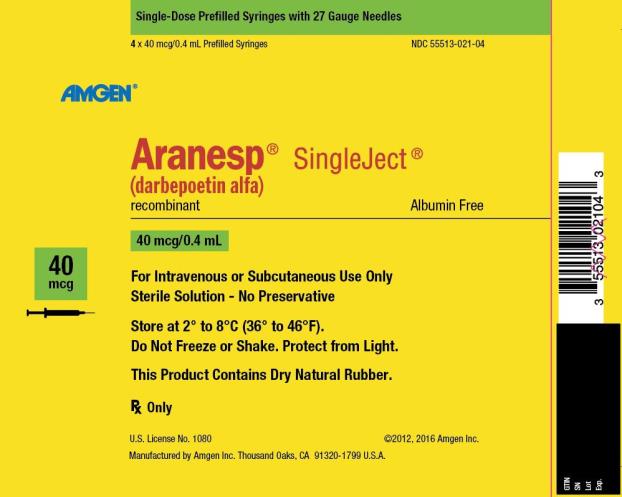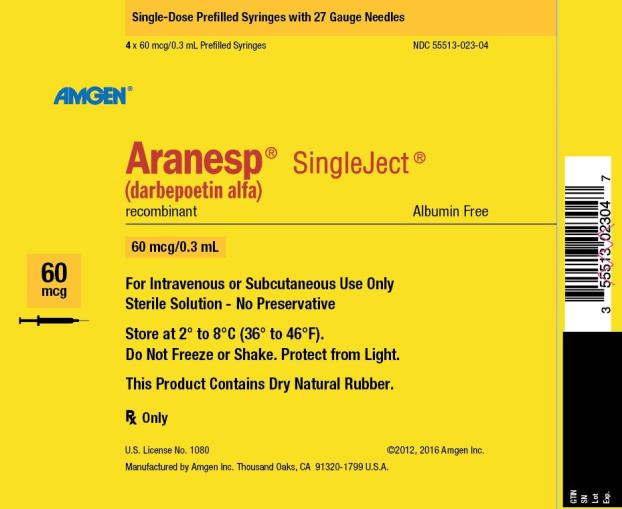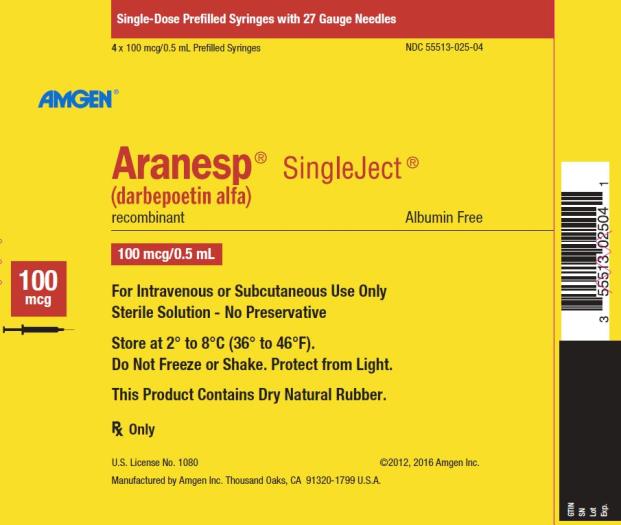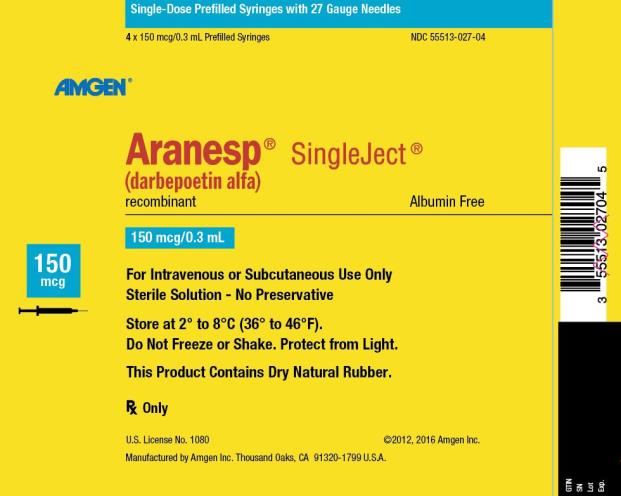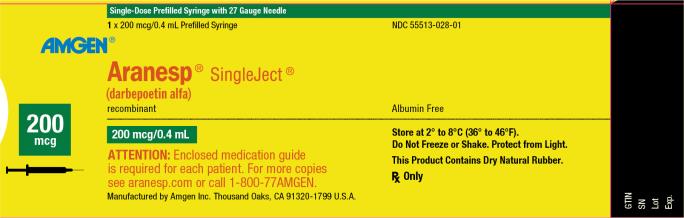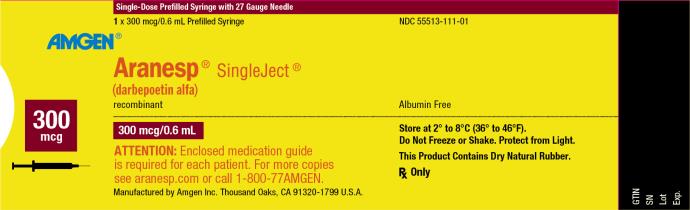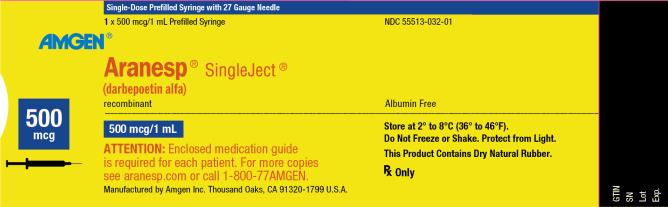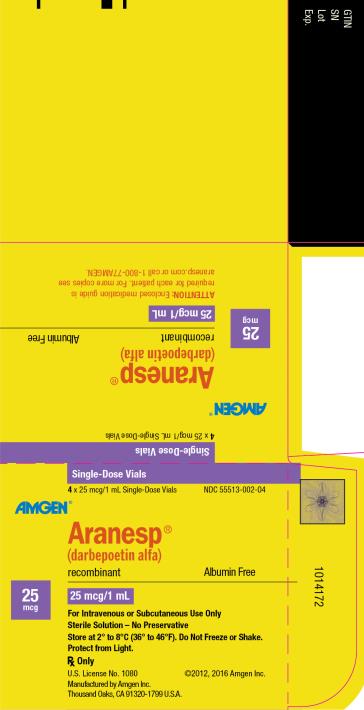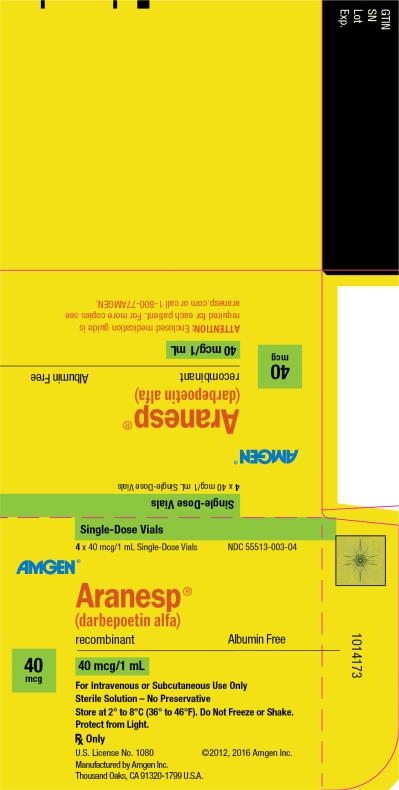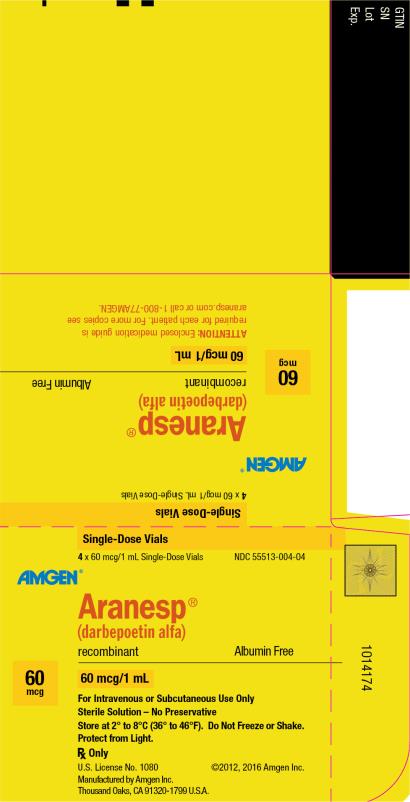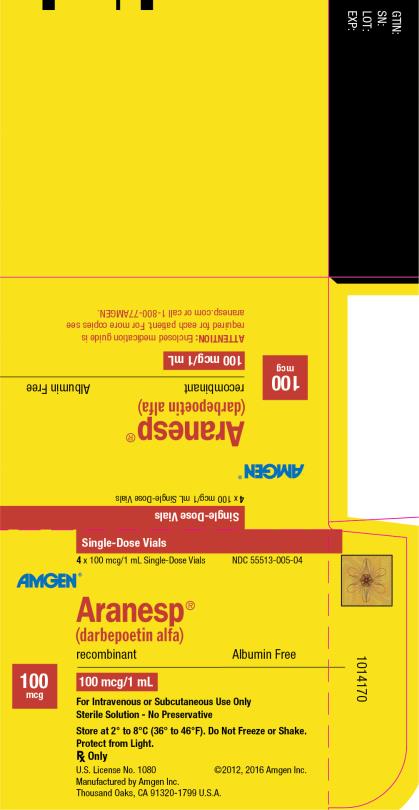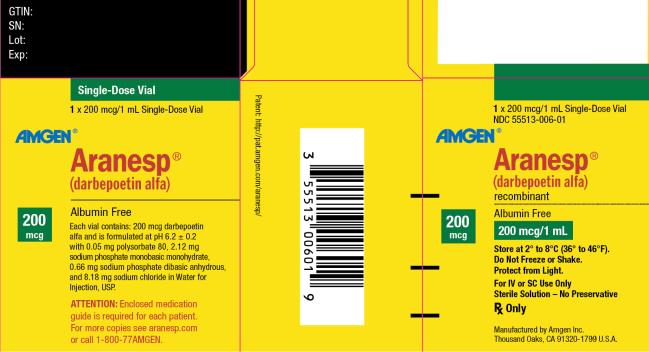 DRUG LABEL: ARANESP
NDC: 55513-098 | Form: INJECTION, SOLUTION
Manufacturer: Amgen Inc
Category: prescription | Type: HUMAN PRESCRIPTION DRUG LABEL
Date: 20241206

ACTIVE INGREDIENTS: DARBEPOETIN ALFA 10 ug/0.4 mL
INACTIVE INGREDIENTS: POLYSORBATE 80 0.02 mg/0.4 mL; SODIUM CHLORIDE 3.44 mg/0.4 mL; WATER; SODIUM PHOSPHATE, DIBASIC, ANHYDROUS 0.28 mg/0.4 mL; SODIUM PHOSPHATE, MONOBASIC, MONOHYDRATE 0.89 mg/0.4 mL

HIGHLIGHTS OF PRESCRIBING INFORMATION

These highlights do not include all the information needed to use ARANESP safely and effectively. See full prescribing information for ARANESP.
ARANESP® (darbepoetin alfa) injection, for intravenous or subcutaneous use
Initial U.S. Approval: 2001

WARNING: ESAs INCREASE THE RISK OF DEATH, MYOCARDIAL INFARCTION, STROKE, VENOUS THROMBOEMBOLISM, THROMBOSIS OF VASCULAR ACCESS AND TUMOR PROGRESSION OR RECURRENCE

See full prescribing information for complete boxed warning.

Chronic Kidney Disease:

- In controlled trials, patients experienced greater risks for death, serious adverse cardiovascular reactions, and stroke when administered erythropoiesis-stimulating agents (ESAs) to target a hemoglobin level of greater than 11 g/dL (5.1).
- No trial has identified a hemoglobin target level, Aranesp dose, or dosing strategy that does not increase these risks (2.2).
- Use the lowest Aranesp dose sufficient to reduce the need for red blood cell (RBC) transfusions (5.1).

Cancer:

- ESAs shortened overall survival and/or increased the risk of tumor progression or recurrence in clinical studies of patients with breast, non-small cell lung, head and neck, lymphoid, and cervical cancers (5.2).
- Use the lowest dose to avoid RBC transfusions (2.3).
- Use ESAs only for anemia from myelosuppressive chemotherapy (1.2).
- ESAs are not indicated for patients receiving myelosuppressive chemotherapy when the anticipated outcome is cure (1.3).
- Discontinue following the completion of a chemotherapy course (2.3).

1 INDICATIONS AND USAGE

Aranesp is an erythropoiesis-stimulating agent (ESA) indicated for the treatment of anemia due to:

- Chronic Kidney Disease (CKD) in patients on dialysis and patients not on dialysis (1.1).
- The effects of concomitant myelosuppressive chemotherapy, and upon initiation, there is a minimum of two additional months of planned chemotherapy (1.2).

Limitations of Use
Aranesp has not been shown to improve quality of life, fatigue, or patient well-being (1.3).

Aranesp is not indicated for use:

- In patients with cancer receiving hormonal agents, biologic products, or radiotherapy, unless also receiving concomitant myelosuppressive chemotherapy (1.3).
- In patients with cancer receiving myelosuppressive chemotherapy when the anticipated outcome is cure (1.3).
- In patients with cancer receiving myelosuppressive chemotherapy in whom the anemia can be managed by transfusion (1.3).
- As a substitute for RBC transfusions in patients who require immediate correction of anemia (1.3).

2 DOSAGE AND ADMINISTRATION

- Recommended starting dose for patients with CKD on dialysis (2.2):
  - 0.45 mcg/kg intravenously or subcutaneously weekly, or
  - 0.75 mcg/kg intravenously or subcutaneously every 2 weeks
  - Intravenous route is recommended for patients on hemodialysis
- Recommended starting dose for patients with CKD not on dialysis (2.2):
  - 0.45 mcg/kg intravenously or subcutaneously at 4 week intervals
- Recommended starting dose for pediatric patients with CKD:
  - 0.45 mcg/kg intravenously or subcutaneously weekly
  - patients with CKD not on dialysis may also be initiated at 0.75 mcg/kg every 2 weeks
- Recommended starting dose for patients with cancer on chemotherapy (2.3):
  - 2.25 mcg/kg subcutaneously weekly, or
  - 500 mcg subcutaneously every 3 weeks

3 DOSAGE FORMS AND STRENGTHS

Single-dose vials

- Injection: 25 mcg, 40 mcg, 60 mcg, 100 mcg, and 200 mcg (3).

Single-dose prefilled syringes

- Injection: 10 mcg/0.4 mL, 25 mcg/0.42 mL, 40 mcg/0.4 mL,
  60 mcg/0.3 mL, 100 mcg/0.5 mL, 150 mcg/0.3 mL, 200 mcg/0.4 mL,
  300 mcg/0.6 mL, and 500 mcg/1 mL (3).

4 CONTRAINDICATIONS

- Uncontrolled hypertension (4)
- Pure red cell aplasia (PRCA) that begins after treatment with Aranesp or other erythropoietin protein drugs (4)
- Serious allergic reactions to Aranesp (4)

5 WARNINGS AND PRECAUTIONS

- Increased Mortality, Myocardial Infarction, Stroke, and Thromboembolism: Using Aranesp to target a hemoglobin level of greater than 11 g/dL increases the risk of serious adverse cardiovascular reactions and has not been shown to provide additional benefit (5.1 and 14.1). Use caution in patients with coexistent cardiovascular disease and stroke (5.1).
- Increased Mortality and/or Increased Risk of Tumor Progression or Recurrence in Patients with Cancer (5.2).
- Hypertension: Control hypertension prior to initiating and during treatment with Aranesp (5.3).
- Seizures: Aranesp increases the risk for seizures in patients with CKD (5.4). Increase monitoring of these patients for changes in seizure frequency or premonitory symptoms (5.4).
- PRCA: If severe anemia and low reticulocyte count develop during Aranesp treatment, withhold Aranesp and evaluate for PRCA (5.6).
- Serious Allergic Reactions: Discontinue Aranesp and manage reactions (5.7).
- Severe Cutaneous Reactions: Discontinue Aranesp (5.8).

6 ADVERSE REACTIONS

- Patients with CKD: Adverse reactions in ≥ 10% of Aranesp-treated patients in clinical studies were hypertension, dyspnea, peripheral edema, cough, and procedural hypotension (6.1).
- Patients with Cancer Receiving Chemotherapy: Adverse reactions in ≥ 1% of Aranesp-treated patients in clinical studies were abdominal pain, edema, and thrombovascular events (6.1).

To report SUSPECTED ADVERSE REACTIONS, contact Amgen Medical Information at 1-800-77-AMGEN (1-800-772-6436) or FDA at 1-800-FDA-1088 or www.fda.gov/medwatch.

FULL PRESCRIBING INFORMATION

WARNING: ESAs INCREASE THE RISK OF DEATH, MYOCARDIAL INFARCTION, STROKE, VENOUS THROMBOEMBOLISM, THROMBOSIS OF VASCULAR ACCESS AND TUMOR PROGRESSION OR RECURRENCE

Chronic Kidney Disease:

- In controlled trials, patients experienced greater risks for death, serious adverse cardiovascular reactions, and stroke when administered erythropoiesis-stimulating agents (ESAs) to target a hemoglobin level of greater than 11 g/dL [see Warnings and Precautions (5.1)].
- No trial has identified a hemoglobin target level, Aranesp dose, or dosing strategy that does not increase these risks [see Dosage and Administration (2.2)].
- Use the lowest Aranesp dose sufficient to reduce the need for red blood cell (RBC) transfusions [see Warnings and Precautions (5.1)].

Cancer:

- ESAs shortened overall survival and/or increased the risk of tumor progression or recurrence in clinical studies of patients with breast, non-small cell lung, head and neck, lymphoid, and cervical cancers [see Warnings and Precautions (5.2)].
- To decrease these risks, as well as the risk of serious cardiovascular and thromboembolic reactions, use the lowest dose needed to avoid RBC transfusions [see Dosage and Administration (2.3)].
- Use ESAs only for anemia from myelosuppressive chemotherapy [see Indications and Usage (1.2)].
- ESAs are not indicated for patients receiving myelosuppressive chemotherapy when the anticipated outcome is cure [see Indications and Usage (1.3)].
- Discontinue following the completion of a chemotherapy course [see Dosage and Administration (2.3)].

1 INDICATIONS AND USAGE

1.1 Anemia Due to Chronic Kidney Disease

Aranesp is indicated for the treatment of anemia due to chronic kidney disease (CKD), including patients on dialysis and patients not on dialysis.

1.2 Anemia Due to Chemotherapy in Patients with Cancer

Aranesp is indicated for the treatment of anemia in patients with non-myeloid malignancies where anemia is due to the effect of concomitant myelosuppressive chemotherapy, and upon initiation, there is a minimum of two additional months of planned chemotherapy.

1.3 Limitations of Use

Aranesp has not been shown to improve quality of life, fatigue, or patient well-being.

Aranesp is not indicated for use:

• In patients with cancer receiving hormonal agents, biologic products, or radiotherapy, unless also receiving concomitant myelosuppressive chemotherapy.

• In patients with cancer receiving myelosuppressive chemotherapy when the anticipated outcome is cure.

• In patients with cancer receiving myelosuppressive chemotherapy in whom the anemia can be managed by transfusion.

• As a substitute for RBC transfusions in patients who require immediate correction of anemia.

2 DOSAGE AND ADMINISTRATION

2.1 Important Dosing Information

Evaluation of Iron Stores and Nutritional Factors

Evaluate the iron status in all patients before and during treatment. Administer supplemental iron therapy when serum ferritin is less than 100 mcg/L or when serum transferrin saturation is less than 20%. The majority of patients with CKD will require supplemental iron during the course of ESA therapy.

Monitoring of Response to Therapy

Correct or exclude other causes of anemia (e.g., vitamin deficiency, metabolic or chronic inflammatory conditions, bleeding, etc.) before initiating Aranesp. Following initiation of therapy and after each dose adjustment, monitor hemoglobin weekly until the hemoglobin level is stable and sufficient to minimize the need for RBC transfusion.

2.2 Patients with Chronic Kidney Disease

In controlled trials, patients experienced greater risks for death, serious adverse cardiovascular reactions, and stroke when administered erythropoiesis-stimulating agents (ESAs) to target a hemoglobin level of greater than 11 g/dL. No trial has identified a hemoglobin target level, Aranesp dose, or dosing strategy that does not increase these risks. Individualize dosing and use the lowest dose of Aranesp sufficient to reduce the need for RBC transfusions [see Warnings and Precautions (5.1)]. Physicians and patients should weigh the possible benefits of decreasing transfusions against the increased risks of death and other serious cardiovascular adverse events [see Boxed Warning and Clinical Studies (14)].

For all patients with CKD

When initiating or adjusting therapy, monitor hemoglobin levels at least weekly until stable, then monitor at least monthly. When adjusting therapy consider hemoglobin rate of rise, rate of decline, ESA responsiveness and hemoglobin variability. A single hemoglobin excursion may not require a dosing change.

- Do not increase the dose more frequently than once every 4 weeks. Decreases in dose can occur more frequently. Avoid frequent dose adjustments.
- If the hemoglobin rises rapidly (e.g., more than 1 g/dL in any 2-week period), reduce the dose of Aranesp by 25% or more as needed to reduce rapid responses.
- For patients who do not respond adequately, if the hemoglobin has not increased by more than 1 g/dL after 4 weeks of therapy, increase the dose by 25%.
- For patients who do not respond adequately over a 12-week escalation period, increasing the Aranesp dose further is unlikely to improve response and may increase risks. Use the lowest dose that will maintain a hemoglobin level sufficient to reduce the need for RBC transfusions. Evaluate other causes of anemia. Discontinue Aranesp if responsiveness does not improve.

For adult patients with CKD on dialysis:

- Initiate Aranesp treatment when the hemoglobin level is less than 10 g/dL.
- If the hemoglobin level approaches or exceeds 11 g/dL, reduce or interrupt the dose of Aranesp.
- The recommended starting dose is 0.45 mcg/kg intravenously or subcutaneously as a weekly injection or 0.75 mcg/kg once every 2 weeks as appropriate. The intravenous route is recommended for patients on hemodialysis.

For adult patients with CKD not on dialysis:

- Consider initiating Aranesp treatment only when the hemoglobin level is less than 10 g/dL and the following considerations apply:
  ° The rate of hemoglobin decline indicates the likelihood of requiring a RBC transfusion and,
  ° Reducing the risk of alloimmunization and/or other RBC transfusion-related risks is a goal.
- If the hemoglobin level exceeds 10 g/dL, reduce or interrupt the dose of Aranesp, and use the lowest dose of Aranesp sufficient to reduce the need for RBC transfusions.
- The recommended starting dose is 0.45 mcg/kg body weight intravenously or subcutaneously given once at four week intervals as appropriate.

For pediatric patients with CKD:

- Initiate Aranesp treatment when the hemoglobin level is less than 10 g/dL.
- If the hemoglobin level approaches or exceeds 12 g/dL, reduce or interrupt the dose of Aranesp.
- The recommended starting dose for pediatric patients (less than 18 years) is 0.45 mcg/kg body weight administered as a single subcutaneous or intravenous injection once weekly; patients not receiving dialysis may be initiated at a dose of 0.75 mcg/kg once every 2 weeks.

When treating patients who have chronic kidney disease and cancer, physicians should refer to Warnings and Precautions (5.1 and 5.2).

Conversion from Epoetin alfa to Aranesp in patients with CKD on dialysis

Aranesp is administered less frequently than epoetin alfa.

- Administer Aranesp once weekly in patients who were receiving epoetin alfa 2 to 3 times weekly.
- Administer Aranesp once every 2 weeks in patients who were receiving epoetin alfa once weekly.

Estimate the starting weekly dose of Aranesp for adults and pediatric patients on the basis of the weekly epoetin alfa dose at the time of substitution (see Table 1). Maintain the route of administration (intravenous or subcutaneous injection).

Table 1. Estimated Aranesp Starting Doses (mcg/week) for Patients with CKD on Dialysis Based on Previous Epoetin alfa Dose (Units/week)
Previous Weekly Epoetin alfa Dose (Units/week) | Aranesp Dose (mcg/week)
 | Adult | Pediatric
< 1,500 | 6.25 | *
1,500 to 2,499 | 6.25 | 6.25
2,500 to 4,999 | 12.5 | 10
5,000 to 10,999 | 25 | 20
11,000 to 17,999 | 40 | 40
18,000 to 33,999 | 60 | 60
34,000 to 89,999 | 100 | 100
≥ 90,000 | 200 | 200

*For pediatric patients receiving a weekly epoetin alfa dose of < 1,500 Units/week, the available data are insufficient to determine an Aranesp conversion dose.

Conversion from Epoetin alfa to Aranesp in patients with CKD not on dialysis

Refer to Table 1. The dose conversion depicted in Table 1 does not accurately estimate the once monthly dose of Aranesp.

2.3 Patients on Cancer Chemotherapy

Initiate Aranesp in patients on cancer chemotherapy only if the hemoglobin is less than 10 g/dL, and if there is a minimum of two additional months of planned chemotherapy.

Use the lowest dose of Aranesp necessary to avoid RBC transfusions.

Recommended Starting Dose

The recommended starting dose and schedules are:

- 2.25 mcg/kg every week subcutaneously until completion of a chemotherapy course.
- 500 mcg every 3 weeks subcutaneously until completion of a chemotherapy course.

Table 2. Dose Adjustment
Dose Adjustment | Weekly Schedule | Every 3 Week Schedule
- If hemoglobin increases greater than 1 g/dL in any 2-week period or - If hemoglobin reaches a level needed to avoid RBC transfusion | Reduce dose by 40% | Reduce dose by 40%
If hemoglobin exceeds a level needed to avoid RBC transfusion | - Withhold dose until hemoglobin approaches a level where RBC transfusions may be required - Reinitiate at a dose 40% below the previous dose | - Withhold dose until hemoglobin approaches a level where RBC transfusions may be required - Reinitiate at a dose 40% below the previous dose
If hemoglobin increases by less than 1 g/dL and remains below 10 g/dL after 6 weeks of therapy | Increase dose to 4.5 mcg/kg/week | No dose adjustment
- If there is no response as measured by hemoglobin levels or if RBC transfusions are still required after 8 weeks of therapy - Following completion of a chemotherapy course | Discontinue Aranesp | Discontinue Aranesp

2.4 Preparation and Administration

- The needle cover of the prefilled syringe contains dry natural rubber (a derivative of latex), which may cause allergic reactions.
- Do not shake. Do not use Aranesp that has been shaken or frozen.
- Protect vials and prefilled syringes from light.
- Parenteral drug products should be inspected visually for particulate matter and discoloration prior to administration. Do not use any vials or prefilled syringes exhibiting particulate matter or discoloration.
- Discard unused portion of Aranesp in vials or prefilled syringes. Do not re-enter vial.
- Do not dilute Aranesp and do not administer in conjunction with other drug solutions.

Self-Administration of the Prefilled Syringe

- Training should aim to demonstrate to those patients and caregivers how to measure the dose of Aranesp, and the focus should be on ensuring that a patient or caregiver can successfully perform all of the steps in the Instructions for Use for a prefilled syringe. If a patient or caregiver is not able to demonstrate that they can measure the dose and administer the product successfully, you should consider whether the patient is an appropriate candidate for self-administration of Aranesp or whether the patient would benefit from a different Aranesp presentation. If a patient or caregiver experiences difficulty measuring the required dose, especially if it is other than the entire contents of the Aranesp prefilled syringe, use of the Aranesp vial may be considered.

3 DOSAGE FORMS AND STRENGTHS

Aranesp is a clear, colorless solution available as:

Single-dose vials

- Injection: 25 mcg, 40 mcg, 60 mcg, 100 mcg, and 200 mcg

Single-dose prefilled syringes

- Injection: 10 mcg/0.4 mL, 25 mcg/0.42 mL, 40 mcg/0.4 mL, 60 mcg/0.3 mL, 100 mcg/0.5 mL,
  150 mcg/0.3 mL, 200 mcg/0.4 mL, 300 mcg/0.6 mL, and 500 mcg/1 mL

4 CONTRAINDICATIONS

Aranesp is contraindicated in patients with:

- Uncontrolled hypertension [see Warnings and Precautions (5.3)].
- Pure red cell aplasia (PRCA) that begins after treatment with Aranesp or other erythropoietin protein drugs [see Warnings and Precautions (5.6)].
- Serious allergic reactions to Aranesp [see Warnings and Precautions (5.7)].

5 WARNINGS AND PRECAUTIONS

5.1 Increased Mortality, Myocardial Infarction, Stroke, and Thromboembolism

- In controlled clinical trials of patients with CKD comparing higher hemoglobin targets (13 - 14 g/dL) to lower targets (9 - 11.3 g/dL), Aranesp and other ESAs increased the risk of death, myocardial infarction, stroke, congestive heart failure, thrombosis of hemodialysis vascular access, and other thromboembolic events in the higher target groups.
- Using Aranesp to target a hemoglobin level of greater than 11 g/dL increases the risk of serious adverse cardiovascular reactions and has not been shown to provide additional benefit [see Clinical Studies (14.1)]. Use caution in patients with coexistent cardiovascular disease and stroke [see Dosage and Administration (2.2)]. Patients with CKD and an insufficient hemoglobin response to ESA therapy may be at even greater risk for cardiovascular reactions and mortality than other patients. A rate of hemoglobin rise of greater than 1 g/dL over 2 weeks may contribute to these risks.
- In controlled clinical trials of patients with cancer, Aranesp and other ESAs increased the risks for death and serious adverse cardiovascular reactions. These adverse reactions included myocardial infarction and stroke.
- In controlled clinical trials, ESAs increased the risk of death in patients undergoing coronary artery bypass graft surgery (CABG) and the risk of deep venous thrombosis (DVT) in patients undergoing orthopedic procedures.

The design and overall results of the 3 large trials comparing higher and lower hemoglobin targets are shown in Table 3.

Table 3. Randomized Controlled Trials Showing Adverse Cardiovascular Outcomes in Patients with CKD
 | Normal Hematocrit Study (NHS) (N = 1265) | CHOIR (N = 1432) | TREAT (N = 4038)
Time Period of Trial | 1993 to 1996 | 2003 to 2006 | 2004 to 2009
Population | Adult patients with CKD on hemodialysis with coexisting CHF or CAD, hematocrit 30 ± 3% on epoetin alfa | Adult patients with CKD not on dialysis with hemoglobin < 11 g/dL not previously administered epoetin alfa | Adult patients with CKD not on dialysis with type II diabetes, hemoglobin ≤ 11 g/dL
Hemoglobin Target; Higher vs. Lower (g/dL) | 14.0 vs. 10.0 | 13.5 vs. 11.3 | 13.0 vs. ≥ 9.0
Median (Q1, Q3) Achieved Hemoglobin level (g/dL) | 12.6 (11.6, 13.3) vs. 10.3 (10.0, 10.7) | 13.0 (12.2, 13.4) vs. 11.4 (11.1, 11.6) | 12.5 (12.0, 12.8) vs. 10.6 (9.9, 11.3)
Primary Endpoint | All-cause mortality or non-fatal MI | All-cause mortality, MI, hospitalization for CHF, or stroke | All-cause mortality, MI, myocardial ischemia, heart failure, and stroke
Hazard Ratio or Relative Risk (95% CI) | 1.28 (1.06 - 1.56) | 1.34 (1.03 - 1.74) | 1.05 (0.94 - 1.17)
Adverse Outcome for Higher Target Group | All-cause mortality | All-cause mortality | Stroke
Hazard Ratio or Relative Risk (95% CI) | 1.27 (1.04 - 1.54) | 1.48 (0.97 - 2.27) | 1.92 (1.38 - 2.68)

Patients with Chronic Kidney Disease

Normal Hematocrit Study (NHS): A prospective, randomized, open-label study of 1265 patients with chronic kidney disease on dialysis with documented evidence of congestive heart failure or ischemic heart disease was designed to test the hypothesis that a higher target hematocrit (Hct) would result in improved outcomes compared with a lower target Hct. In this study, patients were randomized to epoetin alfa treatment targeted to a maintenance hemoglobin of either 14 ± 1 g/dL or 10 ± 1 g/dL. The trial was terminated early with adverse safety findings of higher mortality in the high hematocrit target group. Higher mortality (35% vs. 29%) was observed for the patients randomized to a target hemoglobin of 14 g/dL than for the patients randomized to a target hemoglobin of 10 g/dL. For all-cause mortality, the HR = 1.27; 95% CI (1.04, 1.54); p = 0.018. The incidence of nonfatal myocardial infarction, vascular access thrombosis, and other thrombotic events was also higher in the group randomized to a target hemoglobin of 14 g/dL.

CHOIR: A randomized, prospective trial, 1432 patients with anemia due to CKD who were not undergoing dialysis and who had not previously received epoetin alfa therapy were randomized to epoetin alfa treatment targeting a maintenance hemoglobin concentration of either 13.5 g/dL or 11.3 g/dL. The trial was terminated early with adverse safety findings. A major cardiovascular event (death, myocardial infarction, stroke, or hospitalization for congestive heart failure) occurred in 125 of the 715 patients (18%) in the higher hemoglobin group compared to 97 of the 717 patients (14%) in the lower hemoglobin group [hazard ratio (HR) 1.34, 95% CI: 1.03, 1.74; p = 0.03].

TREAT: A randomized, double-blind, placebo-controlled, prospective trial of 4038 patients with CKD not on dialysis (eGFR of 20 – 60 mL/min), anemia (hemoglobin levels ≤ 11 g/dL), and type 2 diabetes mellitus, patients were randomized to receive either Aranesp treatment or a matching placebo. Placebo group patients also received Aranesp when their hemoglobin levels were below 9 g/dL. The trial objectives were to demonstrate the benefit of Aranesp treatment of the anemia to a target hemoglobin level of 13 g/dL, when compared to a "placebo" group, by reducing the occurrence of either of two primary endpoints: (1) a composite cardiovascular endpoint of all-cause mortality or a specified cardiovascular event (myocardial ischemia, CHF, MI, and CVA) or (2) a composite renal endpoint of all-cause mortality or progression to end stage renal disease. The overall risks for each of the two primary endpoints (the cardiovascular composite and the renal composite) were not reduced with Aranesp treatment (see Table 3), but the risk of stroke was increased nearly two-fold in the Aranesp-treated group versus the placebo group: annualized stroke rate 2.1% vs. 1.1%, respectively, HR 1.92; 95% CI: 1.38, 2.68; p < 0.001. The relative risk of stroke was particularly high in patients with a prior stroke: annualized stroke rate 5.2% in the Aranesp treated group and 1.9% in the placebo group, HR 3.07; 95% CI: 1.44, 6.54. Also, among Aranesp-treated subjects with a past history of cancer, there were more deaths due to all causes and more deaths adjudicated as due to cancer, in comparison with the control group.

Patients with Cancer

An increased incidence of thromboembolic reactions, some serious and life-threatening, occurred in patients with cancer treated with ESAs.

In a randomized, placebo-controlled study (Study 2 in Table 4 [see Warnings and Precautions (5.2)]) of 939 women with metastatic breast cancer receiving chemotherapy, patients received either weekly epoetin alfa or placebo for up to a year. This study was designed to show that survival was superior when epoetin alfa was administered to prevent anemia (maintain hemoglobin levels between 12 and 14 g/dL or hematocrit between 36% and 42%). This study was terminated prematurely when interim results demonstrated a higher mortality at 4 months (8.7% vs. 3.4%) and a higher rate of fatal thrombotic reactions (1.1% vs. 0.2%) in the first 4 months of the study among patients treated with epoetin alfa. Based on Kaplan-Meier estimates, at the time of study termination, the 12-month survival was lower in the epoetin alfa group than in the placebo group (70% vs. 76%; HR 1.37, 95% CI: 1.07, 1.75; p = 0.012).

Patients Having Surgery

Aranesp is not approved for reduction of RBC transfusions in patients scheduled for surgical procedures.

An increased incidence of DVT in patients receiving epoetin alfa undergoing surgical orthopedic procedures was demonstrated. In a randomized, controlled study, 680 adult patients, not receiving prophylactic anticoagulation and undergoing spinal surgery, received epoetin alfa and standard of care (SOC) treatment (n = 340) or SOC treatment alone (n = 340). A higher incidence of DVTs, determined by either color flow duplex imaging or by clinical symptoms, was observed in the epoetin alfa group (16 [4.7%] patients) compared with the SOC group (7 [2.1%] patients). In addition to the 23 patients with DVTs included in the primary analysis, 19 [2.8%] patients experienced 1 other thrombovascular event (TVE) each (12 [3.5%] in the epoetin alfa group and 7 [2.1%] in the SOC group).

Increased mortality was observed in a randomized, placebo-controlled study of epoetin alfa in adult patients who were undergoing CABG surgery (7 deaths in 126 patients randomized to epoetin alfa versus no deaths among 56 patients receiving placebo). Four of these deaths occurred during the period of study drug administration and all 4 deaths were associated with thrombotic events.

5.2 Increased Mortality and/or Increased Risk of Tumor Progression or Recurrence in Patients with Cancer

ESAs resulted in decreased locoregional control/progression-free survival (PFS) and/or overall survival (OS) (see Table 4).

Adverse effects on PFS and/or OS were observed in studies of patients receiving chemotherapy for breast cancer (Studies 1, 2, and 4), lymphoid malignancy (Study 3), and cervical cancer (Study 5); in patients with advanced head and neck cancer receiving radiation therapy (Studies 6 and 7), and in patients with non-small cell lung cancer or various malignancies who were not receiving chemotherapy or radiotherapy (Studies 8 and 9).

Table 4. Randomized, Controlled Studies with Decreased Survival and/or Decreased Locoregional Control
Study/Tumor/(n) | Hemoglobin Target | Hemoglobin (Median; Q1, Q3*) | Primary Efficacy Outcome | Adverse Outcome for ESA-containing Arm
Chemotherapy
Study 1 Metastatic breast cancer (n = 2098) | ≤ 12 g/dL† | 11.6 g/dL; 10.7, 12.1 g/dL | Progression-free survival (PFS) | Decreased progression-free and overall survival
Study 2 Metastatic breast cancer (n = 939) | 12-14 g/dL | 12.9 g/dL; 12.2, 13.3 g/dL | 12-month overall survival | Decreased 12-month survival
Study 3 Lymphoid malignancy (n = 344) | 13-15 g/dL (M) 13-14 g/dL (F) | 11 g/dL; 9.8, 12.1 g/dL | Proportion of patients achieving a hemoglobin response | Decreased overall survival
Study 4 Early breast cancer (n = 733) | 12.5-13 g/dL | 13.1 g/dL; 12.5, 13.7 g/dL | Relapse-free and overall survival | Decreased 3-year relapse-free and overall survival
Study 5 Cervical cancer (n = 114) | 12-14 g/dL | 12.7 g/dL; 12.1, 13.3 g/dL | Progression-free and overall survival and locoregional control | Decreased 3-year progression-free and overall survival and locoregional control
Radiotherapy Alone
Study 6 Head and neck cancer (n = 351) | ≥ 15 g/dL (M) ≥ 14 g/dL (F) | Not available | Locoregional progression-free survival | Decreased 5-year locoregional progression-free and overall survival
Study 7 Head and neck cancer (n = 522) | 14-15.5 g/dL | Not available | Locoregional disease control | Decreased locoregional disease control
No Chemotherapy or Radiotherapy
Study 8 Non-small cell lung cancer (n = 70) | 12-14 g/dL | Not available | Quality of life | Decreased overall survival
Study 9 Non-myeloid malignancy (n = 989) | 12-13 g/dL | 10.6 g/dL; 9.4, 11.8 g/dL | RBC transfusions | Decreased overall survival

*Q1 = 25th percentile

Q3 = 75th percentile

†This study did not include a defined hemoglobin target. Doses were titrated to achieve and maintain the lowest hemoglobin level sufficient to avoid transfusion and not to exceed 12 g/dL.

Decreased Overall Survival

Study 2 was described in the previous section [see Warnings and Precautions (5.1)]. Mortality at 4 months (8.7% vs. 3.4%) was significantly higher in the epoetin alfa arm. The most common investigator-attributed cause of death within the first 4 months was disease progression; 28 of 41 deaths in the epoetin alfa arm and 13 of 16 deaths in the placebo arm were attributed to disease progression. Investigator-assessed time to tumor progression was not different between the 2 groups. Survival at 12 months was significantly lower in the epoetin alfa arm (70% vs. 76%; HR 1.37, 95% CI: 1.07, 1.75; p = 0.012).

Study 3 was a randomized, double-blind study (darbepoetin alfa vs. placebo) conducted in 344 anemic patients with lymphoid malignancy receiving chemotherapy. With a median follow-up of 29 months, overall mortality rates were significantly higher among patients randomized to darbepoetin alfa as compared to placebo (HR 1.36, 95% CI: 1.02, 1.82).

Study 8 was a multicenter, randomized, double-blind study (epoetin alfa vs. placebo) in which patients with advanced non-small cell lung cancer receiving only palliative radiotherapy or no active therapy were treated with epoetin alfa to achieve and maintain hemoglobin levels between 12 and 14 g/dL. Following an interim analysis of 70 patients (planned accrual 300 patients), a significant difference in survival in favor of the patients in the placebo arm of the study was observed (median survival 63 vs. 129 days; HR 1.84; p = 0.04).

Study 9 was a randomized, double-blind study (darbepoetin alfa vs. placebo) in 989 anemic patients with active malignant disease, neither receiving nor planning to receive chemotherapy or radiation therapy. There was no evidence of a statistically significant reduction in proportion of patients receiving RBC transfusions. The median survival was shorter in the darbepoetin alfa treatment group than in the placebo group (8 months vs. 10.8 months; HR 1.30, 95% CI: 1.07, 1.57).

Decreased Progression-free Survival and Overall Survival

Study 1 was a randomized, open-label, multicenter study in 2,098 anemic women with metastatic breast cancer, who received first line or second line chemotherapy. This was a non-inferiority study designed to rule out a 15% risk increase in tumor progression or death of epoetin alfa plus standard of care (SOC) as compared with SOC alone. At the time of clinical data cutoff, the median progression-free survival (PFS) per investigator assessment of disease progression was 7.4 months in each arm (HR 1.09, 95% CI: 0.99, 1.20), indicating the study objective was not met. There were more deaths from disease progression in the epoetin alfa plus SOC arm (59% vs. 56%) and more thrombotic vascular events in the epoetin alfa plus SOC arm (3% vs. 1%). At the final analysis, 1653 deaths were reported (79.8% of subjects in the epoetin alfa plus SOC group and 77.8% of subjects in the SOC group). Median overall survival in the epoetin alfa plus SOC group was 17.8 months compared with 18.0 months in the SOC alone group (HR 1.07, 95% CI: 0.97, 1.18).

Study 4 was a randomized, open-label, controlled, factorial design study in which darbepoetin alfa was administered to prevent anemia in 733 women receiving neo-adjuvant breast cancer treatment. A final analysis was performed after a median follow-up of approximately 3 years. The 3-year survival rate was lower (86% vs. 90%; HR 1.42, 95% CI: 0.93, 2.18) and the 3-year relapse-free survival rate was lower (72% vs. 78%; HR 1.33, 95% CI: 0.99, 1.79) in the darbepoetin alfa-treated arm compared to the control arm.

Study 5 was a randomized, open-label, controlled study that enrolled 114 of a planned 460 patients with cervical cancer receiving chemotherapy and radiotherapy. Patients were randomized to receive epoetin alfa to maintain hemoglobin between 12 and 14 g/dL or to RBC transfusion support as needed. The study was terminated prematurely due to an increase in thromboembolic adverse reactions in epoetin alfa-treated patients compared to control (19% vs. 9%). Both local recurrence (21% vs. 20%) and distant recurrence (12% vs. 7%) were more frequent in epoetin alfa-treated patients compared to control. Progression-free survival at 3 years was lower in the epoetin alfa-treated group compared to control (59% vs. 62%; HR 1.06, 95% CI: 0.58, 1.91). Overall survival at 3 years was lower in the epoetin alfa-treated group compared to control (61% vs. 71%; HR 1.28, 95% CI: 0.68, 2.42).

Study 6 was a randomized, placebo-controlled study in 351 patients with head and neck cancer where epoetin beta or placebo was administered to achieve target hemoglobins ≥ 14 and ≥ 15 g/dL for women and men, respectively. Locoregional progression-free survival was significantly shorter in patients receiving epoetin beta (HR 1.62, 95% CI: 1.22, 2.14; p = 0.0008) with medians of 406 days and 745 days in the epoetin beta and placebo arms respectively. Overall survival was significantly shorter in patients receiving epoetin beta (HR 1.39, 95% CI: 1.05, 1.84; p = 0.02).

Decreased Locoregional Control

Study 7 was a randomized, open-label, controlled study conducted in 522 patients with primary squamous cell carcinoma of the head and neck receiving radiation therapy alone (no chemotherapy) who were randomized to receive darbepoetin alfa to maintain hemoglobin levels of 14 to15.5 g/dL or no darbepoetin alfa. An interim analysis performed on 484 patients demonstrated that locoregional control at 5 years was significantly shorter in patients receiving darbepoetin alfa (RR 1.44, 95% CI: 1.06, 1.96; p = 0.02). Overall survival was shorter in patients receiving darbepoetin alfa (RR 1.28, 95% CI: 0.98, 1.68; p = 0.08).

Non-inferiority for Overall Survival and Progression-free Survival

In a randomized, double-blind, placebo-controlled study to demonstrate non-inferiority of overall survival for Aranesp compared to placebo in patients with anemia receiving chemotherapy for the treatment of advanced stage non-small cell lung cancer (NSCLC), a total of 2549 adult patients who were expected to receive ≥ 2 cycles of myelosuppressive chemotherapy and with a hemoglobin (Hb) ≤ 11.0 g/dL, were randomized 2:1 to Aranesp or placebo and treated to a maximum Hb of 12 g/dL.

Non-inferiority of Aranesp versus placebo was shown for overall survival (OS) and progression-free survival (PFS). The study was designed to rule out a 15% risk increase. The median OS for Aranesp versus placebo was 9.5 and 9.3 months, respectively (stratified hazard ratio 0.92; 95% CI: 0.84–1.01). The median PFS was 4.4 and 4.2 months, respectively (stratified hazard ratio 0.96; 95% CI: 0.87–1.05). Aranesp did not demonstrate superiority to placebo for OS or PFS.

Thrombovascular events were more frequent with Aranesp than placebo group (5.3% Aranesp, 4.1% placebo). No new safety signals were identified [see Warnings and Precautions (5.1)].

5.3 Hypertension

Aranesp is contraindicated in patients with uncontrolled hypertension. In Aranesp clinical studies, approximately 40% of patients with CKD required initiation or intensification of antihypertensive therapy during the early phase of treatment. Hypertensive encephalopathy and seizures have been reported in patients with CKD receiving Aranesp.

Appropriately control hypertension prior to initiation of and during treatment with Aranesp. Reduce or withhold Aranesp if blood pressure becomes difficult to control. Advise patients of the importance of compliance with antihypertensive therapy and dietary restrictions [see Patient Counseling Information (17)].

5.4 Seizures

Aranesp increases the risk of seizures in patients with CKD. During the first several months following initiation of Aranesp, monitor patients closely for premonitory neurologic symptoms. Advise patients to contact their healthcare practitioner for new-onset seizures, premonitory symptoms, or change in seizure frequency.

5.5 Lack or Loss of Hemoglobin Response to Aranesp

For lack or loss of hemoglobin response to Aranesp, initiate a search for causative factors (e.g., iron deficiency, infection, inflammation, bleeding). If typical causes of lack or loss of hemoglobin response are excluded, evaluate for PRCA [see Warnings and Precautions (5.6)]. In the absence of PRCA, follow dosing recommendations for management of patients with an insufficient hemoglobin response to Aranesp therapy [see Dosage and Administration (2.2)].

5.6 Pure Red Cell Aplasia

Cases of PRCA and of severe anemia, with or without other cytopenias that arise following the development of neutralizing antibodies to erythropoietin have been reported in patients treated with Aranesp. This has been reported predominantly in patients with CKD receiving ESAs by subcutaneous administration. PRCA has also been reported in patients receiving ESAs for anemia related to hepatitis C treatment (an indication for which Aranesp is not approved).

If severe anemia and low reticulocyte count develop during treatment with Aranesp, withhold Aranesp and evaluate patients for neutralizing antibodies to erythropoietin. Contact Amgen (1-800-77-AMGEN) to perform assays for binding and neutralizing antibodies. Permanently discontinue Aranesp in patients who develop PRCA following treatment with Aranesp or other erythropoietin protein drugs. Do not switch patients to other ESAs.

5.7 Serious Allergic Reactions

Serious allergic reactions, including anaphylactic reactions, angioedema, bronchospasm, skin rash, and urticaria may occur with Aranesp. Immediately and permanently discontinue Aranesp and administer appropriate therapy if a serious allergic or anaphylactic reaction occurs.

5.8 Severe Cutaneous Reactions

Blistering and skin exfoliation reactions including Erythema multiforme and Stevens-Johnson Syndrome (SJS)/Toxic Epidermal Necrolysis (TEN), have been reported in patients treated with ESAs (including Aranesp) in the post-marketing setting. Discontinue Aranesp therapy immediately if a severe cutaneous reaction, such as SJS/TEN, is suspected.

5.9 Dialysis Management

Patients may require adjustments in their dialysis prescriptions after initiation of Aranesp. Patients receiving Aranesp may require increased anticoagulation with heparin to prevent clotting of the extracorporeal circuit during hemodialysis.

6 ADVERSE REACTIONS

The following clinically significant adverse reactions are discussed in greater detail in other sections of the label:

- Increased Mortality, Myocardial Infarction, Stroke, and Thromboembolism [see Warnings and Precautions (5.1)]
- Increased Mortality and/or Increased Risk of Tumor Progression or Recurrence in Patients with Cancer [see Warnings and Precautions (5.2)]
- Hypertension [see Warnings and Precautions (5.3)]
- Seizures [see Warnings and Precautions (5.4)]
- Pure Red Cell Aplasia [see Warnings and Precautions (5.6)]
- Serious Allergic Reactions [see Warnings and Precautions (5.7)]
- Severe Cutaneous Reactions [see Warnings and Precautions (5.8)]

6.1 Clinical Trial Experience

Because clinical trials are conducted under widely varying conditions, adverse reaction rates observed in the clinical trials of a drug cannot be directly compared to rates in the clinical trials of other drugs and may not reflect the rates observed in practice.

Patients with Chronic Kidney Disease

Adult Patients

Adverse reactions were determined based on pooled data from 5 randomized, active-controlled studies of Aranesp with a total of 1357 patients (Aranesp 766, epoetin alfa 591). The median duration of exposure for patients receiving Aranesp was 340 days, with 580 patients exposed for greater than 6 months and 360 patients exposed for greater than 1 year. The median (25th, 75th percentiles) weight-adjusted dose of Aranesp was 0.50 mcg/kg (0.32, 0.81). The median (range) age for patients administered Aranesp was 62 years (18 to 88). In the Aranesp group, 55% were male, 72% were white, 83% were receiving dialysis, and 17% were not receiving dialysis.

Table 5 lists adverse reactions occurring in ≥ 5% of patients treated with Aranesp.

Table 5. Adverse Reactions Occurring in ≥ 5% of Patients with CKD
Adverse Reaction | Patients Treated with Aranesp (n = 766)
Hypertension | 31%
Dyspnea | 17%
Peripheral edema | 17%
Cough | 12%
Procedural hypotension | 10%
Angina pectoris | 8%
Vascular access complications | 8%
Fluid overload | 7%
Rash/Erythema | 5%
Arteriovenous graft thrombosis | 5%

Rates of adverse reactions with Aranesp therapy were similar to those observed with other recombinant erythropoietins in these studies.

Pediatric Patients

Adverse reactions were determined based on pooled data from 2 randomized, controlled trials [see Clinical Studies (14.1)]. In one study, Aranesp was administered to 81 pediatric patients with CKD who had stable hemoglobin concentrations while previously receiving epoetin alfa. In a second study, Aranesp was administered to 114 anemic pediatric patients with CKD receiving or not receiving dialysis for initial treatment of anemia. In these studies, the most frequently reported serious adverse reactions with Aranesp were hypertension and convulsions. The most commonly reported adverse reactions were hypertension, injection site pain, rash, and convulsions. Aranesp administration was discontinued because of injection site pain in 2 patients and hypertension in 3 patients.

Patients with Cancer Receiving Chemotherapy

Adverse reactions were based on data from a randomized, double-blind, placebo-controlled study of Aranesp in 597 patients (Aranesp 301, placebo 296) with extensive stage small cell lung cancer (SCLC) receiving platinum-based chemotherapy. All patients were white, 64% were male, and the median age was 61 years (range: 28 to 82 years); 25% of the study population were from North America, Western Europe, and Australia. Patients received Aranesp at a dose of 300 mcg or placebo weekly for 4 weeks then every 3 weeks for a total of 24 weeks, and the median duration of exposure was 19 weeks (range: 1 to 26 weeks).

Adverse reactions were also based on data from 7 randomized, double-blind, placebo-controlled studies, including the SCLC study described above, that enrolled 2112 patients (Aranesp 1203, placebo 909) with non-myeloid malignancies. Most patients were white (95%), male (52%), and the median age was 63 years (range: 18 to 91 years); 73% of the study population were from North America, Western Europe, and Australia. Dosing and schedules varied by study from once weekly to once every 4 weeks, and the median duration of exposure was 12 weeks (range: 1 to 27 weeks).

Table 6. Thrombovascular Adverse Reactions in Patients Receiving Chemotherapy
 | SCLC Study |  | All Placebo-controlled Studies
Adverse Reaction | Aranesp (n = 301) | Placebo (n = 296) | Aranesp (n = 2888) | Placebo (n = 1742)
Thromboembolic Adverse Reactions, n (%) | 25 (8.3%) | 13 (4.4%) | 147 (5.1%) | 64 (3.7%)
Arterial | 9 (3%) | 3 (1 %) | 33 (1.1%) | 11 (0.6%)
Myocardial infarction | 5 (1.7%) | 0 | 18 (0.6%) | 5 (0.3%)
Venous | 16 (5.3%) | 10 (3.4%) | 118 (4.1%) | 55 (3.2%)
Pulmonary embolism | 5 (1.7%) | 3 (1%) | 43 (1.5%) | 14 (0.8%)
Cerebrovascular disorders* | 14 (4.7%) | 9 (3%) | 38 (1.3%) | 23 (1.3%)

* “Cerebrovascular disorders” encompasses central nervous system (CNS) hemorrhages and cerebrovascular accidents (ischemic and hemorrhagic). Events in this category may also be included under “thromboembolic adverse reactions.”

In addition to the thrombovascular adverse reactions, abdominal pain and edema occurred at a higher incidence in patients taking Aranesp compared to patients on placebo. Among all placebo-controlled studies, abdominal pain (13.2% vs. 9.4%) and edema (12.8% vs. 9.7%) were reported more frequently in patients receiving Aranesp compared to the placebo group. In the SCLC study the incidence of abdominal pain (10.3% vs. 3.4%) and edema (5.6% vs. 5.1%) in the Aranesp-treated patients compared to those receiving placebo.

6.2 Postmarketing Experience

The following adverse reactions have been identified during postmarketing use of Aranesp.

Because postmarketing reporting of adverse reactions is voluntary and from a population of uncertain size, it is not always possible to reliably estimate their frequency or establish a causal relationship to drug exposure.

- Seizures [see Warnings and Precautions (5.4)]
- Pure Red Cell Aplasia [see Warnings and Precautions (5.6)]
- Serious Allergic Reactions [see Warnings and Precautions (5.7)]
- Severe Cutaneous Reactions [see Warnings and Precautions (5.8)]

6.3 Immunogenicity

As with all therapeutic proteins, there is a potential for immunogenicity.

In clinical studies, the percentage of patients with antibodies to Aranesp was examined using the Biacore® assay. Sera from 1501 patients with CKD and 1159 patients with cancer were tested. At baseline, prior to Aranesp treatment, binding antibodies were detected in 59 patients (4%) with CKD and 36 patients with cancer (3%). During Aranesp therapy (range: 22 to 177 weeks), a follow-up sample was taken. One additional patient with CKD and 8 additional patients with cancer developed antibodies capable of binding Aranesp. In two studies of pediatric patients with CKD aged 2-16, 20 of 111 patients with CKD (18%) receiving dialysis and 6 of 69 patients (9%) not receiving dialysis had anti-ESA antibodies at baseline. During therapy, 4 additional patients receiving dialysis and 4 additional patients not receiving dialysis developed antibodies capable of binding Aranesp.

None of the patients had antibodies capable of neutralizing the activity of Aranesp or endogenous erythropoietin at baseline or at end of study. No clinical sequelae consistent with PRCA were associated with the presence of these antibodies.

The incidence of antibody formation is highly dependent on the sensitivity and specificity of the assay. Additionally, the observed incidence of antibody (including neutralizing antibody) positivity in an assay may be influenced by several factors, including assay methodology, sample handling, timing of sample collection, concomitant medications, and underlying disease. For these reasons, comparison of the incidence of antibodies to Aranesp with the incidence of antibodies to other products may be misleading.

Neutralizing antibodies to darbepoetin alfa that cross-react with endogenous erythropoietin and other ESAs can result in PRCA or severe anemia (with or without other cytopenias) [see Warnings and Precautions (5.6)].

8 USE IN SPECIFIC POPULATIONS

8.1 Pregnancy

Risk Summary

The limited available data on Aranesp use in pregnant women are insufficient to determine a drug-associated risk of major birth defects or miscarriage. In animal reproductive and developmental toxicity studies, Aranesp increased early post-implantation loss at doses approximating the clinical recommended starting doses [see Data].

Consider the benefits and risks of Aranesp for the mother and possible risks to the fetus when prescribing Aranesp to a pregnant woman.

The estimated background risk of major birth defects and miscarriage for the indicated population is unknown. All pregnancies have a background risk of birth defect, loss, or other adverse outcomes. In the U.S. general population, the estimated background risks of major birth defects and miscarriage in clinically recognized pregnancies is 2-4% and 15-20%, respectively.

Data

Animal Data

When Aranesp was administered intravenously during organogenesis to pregnant rats (gestational days 6 to 15) and rabbits (gestational days 6 to 18), there was no evidence of embryofetal toxicity or other adverse outcomes at the intravenous doses tested, up to 20 mcg/kg/day. This animal dose level of 20 mcg/kg/day is approximately 20-fold higher than the clinical recommended starting dose, depending on the patient’s treatment indication. Slightly reduced fetal weights were observed when rat and rabbit mothers received doses of 1 mcg/kg or more, causing exaggerated pharmacological effects in both the rat and rabbit dams. This dose of 1 mcg/kg is near the clinical recommended starting dose. While no adverse effects on uterine implantation occurred in animals, in a rat fertility study, there was an increase in early post-implantation loss at doses equal to or greater than 0.5 mcg/kg, administered 3 times weekly. It is not clear whether the increased post-implantation loss reflects a drug effect on the uterine environment or on the conceptus. No significant placental transfer of Aranesp was observed in rats; placental transfer was not evaluated in rabbits.

In a peri/postnatal development study, pregnant female rats received Aranesp intravenously every other day from implantation (day 6) throughout pregnancy and lactation (day 23). The lowest dose tested, 0.5 mcg/kg, did not cause fetal toxicity; this dose is approximately equivalent to the clinical recommended starting dose. At maternal doses of 2.5 mcg/kg and higher, pups had decreased fetal body weights, which correlated with a slight increase in the incidence of fetal deaths, as well as delayed eye opening and delayed preputial separation. The offspring (F1 generation) of the treated rats were observed postnatally; rats from the F1 generation reached maturity and were mated; no Aranesp related effects were apparent for their offspring (F2 generation fetuses).

8.2 Lactation

Risk Summary

There is no information regarding the presence of Aranesp in human milk, the effects on the breastfed child, or the effects on milk production. The developmental and health benefits of breastfeeding should be considered along with the mother’s clinical need for Aranesp and any potential adverse effects on the breastfed child from Aranesp or from the underlying maternal condition.

8.4 Pediatric Use

Pediatric Patients with CKD

The safety and effectiveness of Aranesp in pediatric patients with CKD receiving and not receiving dialysis have been established in the age groups 1 month to 16 years old. No data are available in pediatric patients less than 1 month old. Use of Aranesp in these age groups is supported by evidence from adequate and well-controlled studies of Aranesp in adults with additional data from a randomized trial evaluating two schedules (weekly and every 2 week dosing) in 114 pediatric patients 1 to 16 years of age receiving darbepoetin alfa, and an observational registry study in 319 pediatric patients < 1 to 16 years of age receiving darbepoetin alfa. Aranesp safety and efficacy were similar between adults and pediatric patients with CKD receiving and not receiving dialysis when Aranesp was used for initial treatment of anemia or patients were transitioned from treatment with epoetin alfa to Aranesp [see Adverse Reactions (6.1), Clinical Pharmacology (12.3) and Clinical Studies (14.1)].

Pediatric Patients with Cancer

The safety and efficacy of Aranesp in pediatric patients with cancer have not been established.

8.5 Geriatric Use

Of the 1801 patients with CKD in clinical studies of Aranesp, 44% were age 65 and over, while 17% were age 75 and over. Of the 873 patients in clinical studies receiving Aranesp and concomitant cancer chemotherapy, 45% were age 65 and over, while 14% were age 75 and over. No differences in safety or efficacy were observed between older and younger patients.

9 DRUG ABUSE AND DEPENDENCE

9.1 Controlled Substance

Aranesp contains darbepoetin alfa, which is not a controlled substance.

9.2 Abuse

Abuse is the intentional, non-therapeutic use of a drug, even once, for its desirable psychological or physiological effects. Abuse of Aranesp may be seen in athletes for the effects on erythropoiesis. Abuse of drugs that increase erythropoiesis, such as Aranesp, by healthy persons may lead to life-threatening cardiovascular complications (e.g., stroke, myocardial infarction, or thromboembolism) [see Warnings and Precautions (5.1)].

In animal studies, darbepoetin alfa did not distribute to the CNS nor produce behavioral effects that are consistent with CNS activity.

10 OVERDOSAGE

Aranesp overdosage can cause hemoglobin levels above the desired level, which should be managed with discontinuation or reduction of Aranesp dosage and/or with phlebotomy, as clinically indicated [see Clinical Pharmacology (12.2)]. Cases of severe hypertension have been observed following overdose with ESAs [see Warnings and Precautions (5.3)].

11 DESCRIPTION

Darbepoetin alfa is an erythropoiesis-stimulating protein that is produced in Chinese hamster ovary (CHO) cells by recombinant DNA technology. Darbepoetin alfa is a 165-amino acid protein that differs from recombinant human erythropoietin in containing 5 N-linked oligosaccharide chains, whereas recombinant human erythropoietin contains 3 chains. The 2 additional N-glycosylation sites result from amino acid substitutions in the erythropoietin peptide backbone. The approximate molecular weight of darbepoetin alfa is 37,000 daltons.

Aranesp (darbepoetin alfa) injection is formulated as a sterile, colorless, preservative-free solution containing polysorbate for intravenous or subcutaneous administration. Each 1 mL contains polysorbate 80 (0.05 mg), sodium chloride (8.18 mg), sodium phosphate dibasic anhydrous (0.66 mg), and sodium phosphate monobasic monohydrate (2.12 mg) in Water for Injection, USP (pH 6.2 ± 0.2).

12 CLINICAL PHARMACOLOGY

12.1 Mechanism of Action

Aranesp stimulates erythropoiesis by the same mechanism as endogenous erythropoietin.

12.2 Pharmacodynamics

Increased hemoglobin levels are not generally observed until 2 to 6 weeks after initiating treatment with Aranesp.

12.3 Pharmacokinetics

Adult Patients with CKD

The pharmacokinetics of Aranesp were studied in patients with CKD receiving or not receiving dialysis and patients with cancer receiving chemotherapy.

Following intravenous administration of Aranesp to patients with CKD receiving dialysis, Aranesp serum concentration-time profiles were biphasic, with a distribution half-life of approximately 1.4 hours and a mean terminal half-life (t1/2) of 21 hours. The t1/2 of Aranesp was approximately 3-fold longer than that of epoetin alfa when administered intravenously.

Following subcutaneous administration of Aranesp to patients with CKD (receiving or not receiving dialysis), absorption was slow and Cmax occurred at 48 hours (range: 12 to 72 hours). In patients with CKD receiving dialysis, the average t1/2 was 46 hours (range: 12 to 89 hours), and in patients with CKD not receiving dialysis, the average t1/2 was 70 hours (range: 35 to 139 hours). Aranesp apparent clearance was approximately 1.4 times faster on average in patients receiving dialysis compared to patients not receiving dialysis. The bioavailability of Aranesp in patients with CKD receiving dialysis after subcutaneous administration was 37% (range: 30% to 50%).

Pediatric Patients with CKD

Aranesp pharmacokinetics was evaluated in 12 pediatric patients (age 3 to 16 years) with CKD receiving or not receiving dialysis in one study (n = 12). In a phase 1 pharmacokinetic study, following a single intravenous or subcutaneous Aranesp dose, Cmax and t1/2 were similar to those obtained in adult patients with CKD on dialysis. Additionally, following a single subcutaneous dose, the average bioavailability was 54% (range: 32% to 70%), which was higher than that obtained in adult patients with CKD on dialysis.

Adult Patients with Cancer

Following the first subcutaneous dose of 6.75 mcg/kg (equivalent to 500 mcg for a 74 kg patient) in patients with cancer, the mean t1/2 was 74 hours (range: 24 to 144 hours) and Cmax was observed at 71 hours (range: 28 to 120 hours). When administered on a once every 3 week schedule, 48-hour postdose Aranesp levels after the fourth dose were similar to those after the first dose.

Over the dose range of 0.45 to 4.5 mcg/kg Aranesp administered intravenously or subcutaneously on a once weekly schedule and 4.5 to 15 mcg/kg administered subcutaneously on a once every 3 week schedule, systemic exposure was approximately proportional to dose. No evidence of accumulation was observed beyond an expected less than 2-fold increase in blood levels when compared to the initial dose.

13 NONCLINICAL TOXICOLOGY

13.1 Carcinogenesis, Mutagenesis, Impairment of Fertility

The carcinogenic potential of Aranesp has not been evaluated in long-term animal studies. In toxicity studies of approximately 6 months duration in rats and dogs, no tumorigenic or unexpected mitogenic responses were observed in any tissue type.

Aranesp was not mutagenic or clastogenic under the conditions tested. Aranesp was negative in the in vitro bacterial reverse mutation assay, the in vitro mammalian cell gene mutation assay (using CHO cells), and in the in vivo mouse erythrocyte micronucleus assay.

Aranesp increased the incidence of post-implantation losses in rats. Male and female rats received intravenous doses prior to and during mating; then females were treated 3 times weekly during the first trimester of gestation (gestation days 1, 3, 5, and 7). No effect on reproductive performance, fertility, or sperm assessment parameters were detected at any of the doses evaluated (up to 10 mcg/kg, administered 3 times weekly). The dose of 10 mcg/kg is more than 10-fold higher than the clinical recommended starting dose. An increase in post-implantation fetal loss was seen at doses equal to or greater than 0.5 mcg/kg, administered 3 times weekly. The dose of 0.5 mcg/kg is approximately equivalent to the clinical recommended starting dose. Signs of exaggerated pharmacology were not observed in the mother receiving 0.5 mcg/kg or less, but were observed at 2.5 mcg/kg and higher.

14 CLINICAL STUDIES

Clinical studies in the nephrology and chemotherapy-induced anemia clinical programs are designated with the prefixes “N” and “C”, respectively.

14.1 Patients with Chronic Kidney Disease

Patients with chronic kidney disease on dialysis: ESA effects on rates of transfusion

In early clinical studies conducted in patients with CKD on dialysis, ESAs have been shown to reduce the use of RBC transfusions. These studies enrolled patients with mean baseline hemoglobin levels of approximately 7.5 g/dL and ESAs were generally titrated to achieve a hemoglobin level of approximately 12 g/dL. Fewer transfusions were given during the ESA treatment period when compared to a pre-treatment interval.

In the Normal Hematocrit Study, the yearly transfusion rate was 51.5% in the lower hemoglobin group (10 g/dL) and 32.4% in the higher hemoglobin group (14 g/dL).

Patients with chronic kidney disease not on dialysis: ESA effects on rates of transfusion

In TREAT, a randomized, double-blind trial of 4038 patients with CKD and type 2 diabetes not on dialysis, a post-hoc analysis showed that the proportion of patients receiving RBC transfusions was lower in patients administered Aranesp to target a hemoglobin of 13 g/dL compared to the control arm in which Aranesp was administered intermittently if hemoglobin concentration decreased to less than 9 g/dL (15% versus 25%, respectively). In CHOIR, a randomized open-label study of 1432 patients with CKD not on dialysis, use of an ESA to target a higher (13.5 g/dL) versus lower (11.3 g/dL) hemoglobin goal did not reduce the use of RBC transfusions. In each trial, no benefits occurred for the cardiovascular or end-stage renal disease outcomes. In each trial, the potential benefit of ESA therapy was offset by worse cardiovascular safety outcomes resulting in an unfavorable benefit-risk profile [see Warnings and Precautions (5.1)].

ESA Effects on quality of life

Aranesp use has not been demonstrated in controlled clinical trials to improve quality of life, fatigue, or patient well-being.

ESA Effects on rates of death and other serious cardiac adverse events

Three randomized outcome trials (Normal Hematocrit Study [NHS], Correction of Anemia with Epoetin Alfa in Chronic Kidney Disease [CHOIR], and Trial of Darbepoetin Alfa in Type 2 Diabetes and CKD [TREAT]) have been conducted in patients with CKD using Epogen/PROCRIT/Aranesp to target higher vs. lower hemoglobin levels. Though these trials were designed to establish a cardiovascular or renal benefit of targeting higher hemoglobin levels, in all 3 studies, patients randomized to the higher hemoglobin target experienced worse cardiovascular outcomes and showed no reduction in progression to ESRD. In each trial, the potential benefit of ESA therapy was offset by worse cardiovascular safety outcomes resulting in an unfavorable benefit-risk profile [see Warnings and Precautions (5.1)].

Other ESA trials

Three studies (2 in adults and 1 in pediatric patients) evaluated the safety and efficacy of the de novo use of Aranesp for the correction of anemia in patients with CKD, and 3 studies (2 in adults and 1 in pediatric patients) assessed the ability of Aranesp to maintain hemoglobin concentrations in patients with CKD who had been receiving other recombinant erythropoietins.

De Novo Use of Aranesp

Adult Patients

Once Weekly Aranesp Starting Dose

In 2 randomized, open-label studies, Aranesp or epoetin alfa was administered for the correction of anemia in patients with CKD who had not been receiving prior treatment with exogenous erythropoietin. Study N1 evaluated patients with CKD receiving dialysis; Study N2 evaluated patients not requiring dialysis. In both studies, the starting dose of Aranesp was 0.45 mcg/kg administered once weekly. The starting dose of epoetin alfa was 50 Units/kg 3 times weekly in Study N1 and 50 Units/kg twice weekly in Study N2. When necessary, dosage adjustments were instituted to maintain hemoglobin in the study target range of 11 to 13 g/dL. (Note: The recommended hemoglobin target range is lower than the target range of these studies [see Dosage and Administration (2.2)]). The primary efficacy endpoint was the proportion of patients who experienced at least a 1 g/dL increase in hemoglobin concentration to a level of at least 11 g/dL by 20 weeks (Study N1) or 24 weeks (Study N2). The studies were designed to assess the safety and effectiveness of Aranesp but not to support conclusions regarding comparisons between the 2 products.

In Study N1, the primary efficacy endpoint was achieved by 72% (95% CI: 62%, 81%) of the 90 patients treated with Aranesp and 84% (95% CI: 66%, 95%) of the 31 patients treated with epoetin alfa. The mean increase in hemoglobin over the initial 4 weeks of Aranesp treatment was 1.1 g/dL (95% CI: 0.82 g/dL, 1.37 g/dL).

In Study N2, the primary efficacy endpoint was achieved by 93% (95% CI: 87%, 97%) of the 129 patients treated with Aranesp and 92% (95% CI: 78%, 98%) of the 37 patients treated with epoetin alfa. The mean increase in hemoglobin from baseline through the initial 4 weeks of Aranesp treatment was 1.38 g/dL (95% CI: 1.21 g/dL, 1.55 g/dL).

Once Every 2 Week Aranesp Starting Dose

In 2 single-arm studies (N3 and N4), Aranesp was administered for the correction of anemia in patients with CKD not receiving dialysis. In both studies, the starting dose of Aranesp was 0.75 mcg/kg administered once every 2 weeks.

In Study N3 (study duration of 18 weeks), the hemoglobin goal (hemoglobin concentration ≥ 11 g/dL) was achieved by 92% (95% CI: 86%, 96%) of the 128 patients treated with Aranesp.

In Study N4 (study duration of 24 weeks), the hemoglobin goal (hemoglobin concentration of 11 to 13 g/dL) was achieved by 85% (95% CI: 77%, 93%) of the 75 patients treated with Aranesp.

Pediatric Patients

Study N8 was a double-blind, randomized, controlled study in 114 pediatric patients from 1 to 18 years of age receiving darbepoetin alfa. In this study, pediatric patients with CKD receiving or not receiving dialysis who were anemic (hemoglobin [Hb] < 10.0 g/dL) and not being treated with an erythropoiesis stimulating agent (ESA) received darbepoetin alfa weekly or once every 2 weeks for the correction of anemia.

The primary efficacy endpoint was proportion of patients having hemoglobin corrected to ≥ 10.0 g/dL at any time point after the first dose without receiving any red blood cell transfusions after randomization and within 90 days prior to the Hb measurement. For pediatric patients receiving QW dosing, 98% (95% CI: 91%-100%), had hemoglobin concentrations corrected to ≥ 10 g/dL. For those receiving Q2W dosing, 84% (95% CI: 72%-92%), had hemoglobin concentrations corrected to ≥ 10 g/dL. The study was designed to assess the safety and effectiveness of Aranesp but not to support conclusions regarding comparisons between the 2 regimens.

Conversion from Other Recombinant Erythropoietins

Two studies of adults (N5 and N6) and 1 study in pediatric patients (N7) were conducted in patients who had been receiving other recombinant erythropoietins for treatment of the anemia due to CKD. The studies compared the abilities of Aranesp and other erythropoietins to maintain hemoglobin concentrations within a study target range of 9 to 13 g/dL in adults and 10 to 12.5 g/dL in pediatric patients. (Note: The recommended hemoglobin target is lower than the target range of these studies [see Dosage and Administration (2.2)]). Patients who had been receiving stable doses of other recombinant erythropoietins were randomized to Aranesp or continued with their prior erythropoietin at the previous dose and schedule. For patients randomized to Aranesp, the initial weekly dose was determined on the basis of the previous total weekly dose of recombinant erythropoietin.

Adult Patients

Study N5 was a double-blind study in which 169 hemodialysis patients were randomized to treatment with Aranesp and 338 patients continued on epoetin alfa. Study N6 was an open-label study in which 347 patients were randomized to treatment with Aranesp and 175 patients were randomized to continue on epoetin alfa or epoetin beta. Of the patients randomized to Aranesp, 92% were receiving hemodialysis and 8% were receiving peritoneal dialysis.

In Study N5, a median weekly dose of 0.53 mcg/kg Aranesp (25th, 75th percentiles: 0.30, 0.93 mcg/kg) was required to maintain hemoglobin in the study target range. In Study N6, a median weekly dose of 0.41 mcg/kg Aranesp (25th, 75th percentiles: 0.26, 0.65 mcg/kg) was required to maintain hemoglobin in the study target range.

Pediatric Patients

Study N7 was an open-label, randomized study conducted in the United States in pediatric patients from 1 to 18 years of age with CKD receiving or not receiving dialysis. Eighty-one patients with hemoglobin concentrations that were stable on epoetin alfa received Aranesp (subcutaneously or intravenously), and 42 patients continued to receive epoetin alfa at the current dose, schedule, and route of administration. Patients received Aranesp once weekly if previously receiving epoetin alfa 2 or 3 times weekly or once every other week if previously receiving epoetin alfa weekly. A median weekly dose of 0.41 mcg/kg Aranesp (25th, 75th percentiles: 0.25, 0.82 mcg/kg) was required to maintain hemoglobin in the study target range.

14.2 Patients with Cancer Receiving Chemotherapy

The safety and efficacy of Aranesp was assessed in two multicenter, randomized studies in patients with anemia due to the effect of concomitantly administered cancer chemotherapy. Study C1 was a randomized (1:1), placebo-controlled, double-blind, multinational study conducted in 314 patients where Aranesp was administered weekly. Study C2 was a randomized (1:1), double-blind, double-dummy, active-controlled, multinational study conducted in 705 patients where Aranesp was administered either every week or every 3 weeks. Efficacy was demonstrated by a statistically significant reduction in the proportion of patients receiving RBC transfusions among patients who were on study therapy for more than 28 days.

Study C1

Study C1 was conducted in anemic patients (hemoglobin ≤ 11 g/dL) with non-small cell lung cancer or small cell lung cancer who were scheduled to receive at least 12 weeks of a platinum-containing chemotherapy regimen. Randomization was stratified by tumor type and region (Australia vs. Canada vs. Europe). Patients received Aranesp 2.25 mcg/kg or placebo as a weekly subcutaneous injection commencing on the first day of the chemotherapy cycle. Efficacy was determined by a reduction in the proportion of patients who received RBC transfusions between week 5 (day 29) and end of treatment period (12 weeks) in the subset of 297 randomized patients (148 Aranesp and 149 placebo) who were on-study at the beginning of study week 5. All 297 patients were white, 72% were male, 71% had non-small cell histology, and the median age was 62 years (range: 36 to 80). A significantly lower proportion of patients in the Aranesp arm received RBC transfusions during week 5 to the end of treatment compared to patients in the placebo arm (crude percentages: 26% vs. 50%; p < 0.001, based on a comparison of the difference in Kaplan-Meier proportions using the Cochran-Mantel-Haenszel strata-adjusted Chi-square test).

Study C2

Study C2 was conducted in anemic patients (hemoglobin < 11 g/dL) with non-myeloid malignancies receiving chemotherapy. Randomization was stratified by region (Western vs. Central/Eastern Europe), tumor type (lung and gynecological vs. others), and baseline hemoglobin (< 10 vs. ≥ 10 g/dL); all patients received double-dummy placebo and either Aranesp 500 mcg every 3 weeks or Aranesp 2.25 mcg/kg weekly subcutaneous injections for 15 weeks. Six hundred seventy-one out of 672 patients were white, 55% were female, and the median age was 60 years (range: 20 to 86). One hundred seven patients (16%) had lung or gynecological cancer while 565 (84%) had other tumor types. In both treatment schedules, the dose was reduced by 40% of the previous dose if hemoglobin level increased by more than 1 g/dL in a 14-day period.

Efficacy was determined by a comparison of the proportion of patients who received at least 1 RBC transfusion between week 5 (day 29) and the end of treatment. Three hundred thirty-five patients in the every 3 week dosing arm and 337 patients in the weekly dosing arm remained on study through or beyond day 29 and were evaluable for efficacy. Two hundred thirty-eight patients (71%) in the every 3-week arm and 261 patients (77%) patients in the weekly arm required dose reductions. Twenty-three percent (95% CI: 18%, 28%) of patients in the every 3-week treatment schedule and 28% (95% CI: 24%, 34%) in the weekly schedule received at least 1 RBC transfusion. The observed difference in the RBC transfusion rates (every 3 week minus weekly) was -5.8% (95% CI: -12.4%, 0.8%).

Study C3

Lack of Efficacy in Improving Survival

Study C3 was conducted in patients required to have a hemoglobin concentration ≥ 9 g/dL and ≤ 13 g/dL with previously untreated extensive-stage small cell lung cancer (SCLC) receiving platinum and etoposide chemotherapy. Randomization was stratified by region (Western Europe, Australia/North America, and rest of world), Eastern Cooperative Oncology Group (ECOG) performance status (0 or 1 vs. 2), and lactate dehydrogenase (below vs. above the upper limit of normal). Patients were randomized to receive Aranesp (n = 298) at a dose of 300 mcg once weekly for the first 4 weeks, followed by 300 mcg once every 3 weeks for the remainder of the treatment period or placebo (n = 298).

This study was designed to detect a prolongation in overall survival (from a median of 9 months to a median of 12 months). For the final analysis, there was no evidence of improved survival (p = 0.43, log-rank test).

16 HOW SUPPLIED/STORAGE AND HANDLING

Store at 36°F to 46°F (2°C to 8°C). Do not freeze.

Do not shake. Protect from light; store Aranesp in the carton until use.

Do not use Aranesp that has been shaken or frozen.

Aranesp is a clear, colorless solution available in the following packages:

Single-dose Vial

1 Vial/Pack, 4 Packs/Case | 4 Vials/Pack, 10 Packs/Case
200 mcg/1 mL (NDC 55513-006-01) (NDC 55513-006-21) | 25 mcg/1 mL (NDC 55513-002-04)
 | 40 mcg/1 mL (NDC 55513-003-04)
 | 60 mcg/1 mL (NDC 55513-004-04)
 | 100 mcg/1 mL (NDC 55513-005-04)

Single-dose Prefilled Syringe (SingleJect®) with a 27-gauge, ½-inch needle with an UltraSafe® Needle Guard that is manually activated to cover the needle during disposal

1 Syringe/Pack, 4 Packs/Case | 4 Syringes/Pack, 10 Packs/Case
200 mcg/0.4 mL (NDC 55513-028-01) | 10 mcg/0.4 mL (NDC 55513-098-04)
300 mcg/0.6 mL (NDC 55513-111-01) | 25 mcg/0.42 mL (NDC 55513-057-04)
500 mcg/1 mL (NDC 55513-032-01) | 40 mcg/0.4 mL (NDC 55513-021-04)
 | 60 mcg/0.3 mL (NDC 55513-023-04)
 | 100 mcg/0.5 mL (NDC 55513-025-04)
 | 150 mcg/0.3 mL (NDC 55513-027-04)

17 PATIENT COUNSELING INFORMATION

Advise the patient to read the FDA-approved patient labeling (Medication Guide and Instructions for Use).

Review the steps for direct patient administration with patients and caregivers. Training should aim to ensure that patients and caregivers can successfully perform all of the steps in the Instructions for Use of Aranesp prefilled syringe, including showing the patient or caregiver how to measure the required dose, particularly if a patient is on a dose other than the entire prefilled syringe. If a patient or caregiver is not able to demonstrate that they can measure the dose and administer the product successfully, you should consider whether the patient is an appropriate candidate for self-administration of Aranesp or whether the patient would benefit from a different Aranesp presentation.

Inform patients:

- Of the increased risks of mortality, serious cardiovascular reactions, thromboembolic reactions, stroke, and tumor progression [see Warnings and Precautions (5.1 and 5.2)].
- To undergo regular blood pressure monitoring, adhere to prescribed anti-hypertensive regimen and follow recommended dietary restrictions.
- To contact their healthcare provider for new-onset neurologic symptoms or change in seizure frequency.
- Of the need to have regular laboratory tests for hemoglobin.

Instruct patients who self-administer Aranesp of the:

- Importance of following the Instructions for Use.
- Dangers of reusing needles, syringes, or unused portions of single-dose vials.
- Proper disposal of used syringes, needles, and unused vials, and of the full container.
- Importance of informing healthcare provider if difficulty occurs when measuring or administering partial doses from the Aranesp prefilled syringe. If difficulty occurs, use of other syringes or Aranesp vial may be considered.

ARANESP® (darbepoetin alfa)

Manufactured by:
Amgen Inc.
One Amgen Center Drive
Thousand Oaks, CA 91320-1799 U.S.A.
U.S. License Number 1080
Patent: http://pat.amgen.com/aranesp/

© 2001-2019, 2024 Amgen Inc. All rights reserved.

*UltraSafe® is a registered trademark of Safety Syringes, Inc.

1xxxxxx- v38

MEDICATION GUIDE
ARANESP® (Air-uh-nesp)
(darbepoetin alfa)

Read this Medication Guide:

- before you start Aranesp.
- if you are told by your healthcare provider that there is new information about Aranesp.
- if you are told by your healthcare provider that you may inject Aranesp at home, read this Medication Guide each time you receive a new supply of medicine.

This Medication Guide does not take the place of talking to your healthcare provider about your medical condition or your treatment. Talk with your healthcare provider regularly about the use of Aranesp and ask if there is new information about Aranesp.

What is the most important information I should know about Aranesp?
Aranesp may cause serious side effects that can lead to death, including:
For people with cancer:

- Your tumor may grow faster and you may die sooner if you choose to take Aranesp. Your healthcare provider will talk with you about these risks.

For all people who take Aranesp, including people with cancer or chronic kidney disease:

- Serious heart problems, such as heart attack or heart failure, and stroke. You may die sooner if you are treated with Aranesp to increase red blood cells (RBCs) to near the same level found in healthy people.
- Blood clots. Blood clots may happen at any time while taking Aranesp. If you are receiving Aranesp for any reason and you are going to have surgery, talk to your healthcare provider about whether or not you need to take a blood thinner to lessen the chance of blood clots during or following surgery. Blood clots can form in blood vessels (veins), especially in your leg (deep venous thrombosis or DVT). Pieces of a blood clot may travel to the lungs and block the blood circulation in the lungs (pulmonary embolus).
- Call your healthcare provider or get medical help right away if you have any of these symptoms:
  - Chest pain
  - Trouble breathing or shortness of breath
  - Pain in your legs, with or without swelling
  - A cool or pale arm or leg
  - Sudden confusion, trouble speaking, or trouble understanding others' speech
  - Sudden numbness or weakness in your face, arm, or leg, especially on one side of your body
  - Sudden trouble seeing
  - Sudden trouble walking, dizziness, loss of balance or coordination
  - Loss of consciousness (fainting)
  - Hemodialysis vascular access stops working

See “What are the possible side effects of Aranesp?” below for more information.
If you decide to take Aranesp, your healthcare provider should prescribe the smallest dose of Aranesp that is necessary to reduce your chance of needing red blood cell transfusions.

What is Aranesp?
Aranesp is a prescription medicine used to treat anemia. People with anemia have a lower-than-normal number of RBCs. Aranesp works like the human protein called erythropoietin to help your body make more RBCs. Aranesp is used to reduce or avoid the need for RBC transfusions.
Aranesp may be used to treat anemia if it is caused by:

- Chronic kidney disease (you may or may not be on dialysis).
- Chemotherapy that will be used for at least two months after starting Aranesp.

If your hemoglobin level stays too high or if your hemoglobin goes up too quickly, this may lead to serious health problems which may result in death. These serious health problems may happen if you take Aranesp, even if you do not have an increase in your hemoglobin level.
Aranesp has not been proven to improve the quality of life, fatigue, or well-being.
Aranesp should not be used for the treatment of anemia:

- If you have cancer and you will not be receiving chemotherapy that may cause anemia.
- If you have a cancer that has a high chance of being cured. Talk with your healthcare provider about the kind of cancer you have.
- If your anemia caused by chemotherapy treatment can be managed by RBC transfusion.
- In place of emergency treatment for anemia (RBC transfusions).

It is not known if Aranesp is safe and effective in children who have cancer.

Who should not take Aranesp?
Do not take Aranesp if you:

- Have cancer and have not been counseled by your healthcare provider about treatment with Aranesp.
- Have high blood pressure that is not controlled (uncontrolled hypertension).
- Have been told by your healthcare provider that you have or have ever had a type of anemia called Pure Red Cell Aplasia (PRCA) that starts after treatment with Aranesp or other erythropoietin protein medicines.
- Have had a serious allergic reaction to Aranesp.

Before taking Aranesp, tell your healthcare provider about all of your medical conditions, including if you:

- Have heart disease.
- Have high blood pressure.
- Have had a seizure (convulsion) or stroke.
- Are allergic to latex. The needle cover on the prefilled syringe contains latex.
- Receive dialysis treatment.
- Are pregnant or plan to become pregnant. It is not known if Aranesp may harm your unborn baby. Talk to your healthcare provider about possible pregnancy and birth control choices that are right for you.
- Are breastfeeding or plan to breastfeed. It is not known if Aranesp passes into breast milk.

Tell your healthcare provider about all the medicines you take, including prescription and over-the-counter medicines, vitamins, and herbal supplements.

How should I take Aranesp?

- If you or your caregiver has been trained to give Aranesp shots (injections) at home:
  - Be sure that you read, understand, and follow the "Instructions for Use" that come with Aranesp.
  - Take Aranesp exactly as your healthcare provider tells you to. Do not change the dose of Aranesp unless told to do so by your healthcare provider.
  - Your healthcare provider will show you how much Aranesp to use, how to inject it, how often it should be injected, and how to safely throw away the used vials, syringes, and needles.
  - If you miss a dose of Aranesp, call your healthcare provider right away and ask what to do.
  - If you take more than the prescribed dose of Aranesp, call your healthcare provider right away.
- During treatment with Aranesp, continue to follow your healthcare provider’s instructions for diet and medicines.
- Have your blood pressure checked as instructed by your healthcare provider.

What are the possible side effects of Aranesp?
Aranesp may cause serious side effects, including:

- See “What is the most important information I should know about Aranesp?”
- High blood pressure. High blood pressure is a common side effect of Aranesp in people with chronic kidney disease. Your blood pressure may go up or be difficult to control with blood pressure medicine while taking Aranesp. This can happen even if you have never had high blood pressure before. Your healthcare provider should check your blood pressure often. If your blood pressure does go up, your healthcare provider may prescribe new or more blood pressure medicine.
- Seizures. If you have any seizures while taking Aranesp, get medical help right away and tell your healthcare provider.
- Antibodies to Aranesp. Your body may make antibodies to Aranesp. These antibodies can block or lessen your body’s ability to make RBCs and cause you to have severe anemia. Call your healthcare provider if you have unusual tiredness, lack of energy, dizziness, or fainting. You may need to stop taking Aranesp.
- Serious allergic reactions. Serious allergic reactions can cause a skin rash, itching, shortness of breath, wheezing, dizziness and fainting because of a drop in blood pressure, swelling around your mouth or eyes, fast pulse, or sweating. If you have a serious allergic reaction, stop using Aranesp and call your healthcare provider or get medical help right away.
- Severe skin reactions. Signs and symptoms of severe skin reactions with Aranesp may include: skin rash with itching, blisters, skin sores, peeling or areas of skin coming off. If you have any signs or symptoms of a severe skin reaction, stop using Aranesp and call your healthcare provider or get medical help right away.

Common side effects of Aranesp include:

- shortness of breath
- cough
- low blood pressure during dialysis
- abdominal pain
- edema (swelling) of the arms or legs

These are not all the possible side effects of Aranesp. Your healthcare provider can give you a more complete list. Tell your healthcare provider about any side effects that bother you or that do not go away.
Call your doctor for medical advice about side effects. You may report side effects to FDA at 1-800-FDA-1088.

How should I store Aranesp?

- Do not shake Aranesp.
- Store Aranesp in the carton it comes in to protect it from light.
- Store Aranesp in the refrigerator between 36°F to 46°F (2°C to 8°C).
- Do not freeze Aranesp. Do not use Aranesp that has been frozen.
- Throw away the Aranesp vial or prefilled syringe after one use. Do not re-use even if there is medicine left.

Keep Aranesp and all medicines out of the reach of children.

General information about the safe and effective use of Aranesp.
Medicines are sometimes prescribed for purposes other than those listed in a Medication Guide. Do not use Aranesp for a condition for which it was not prescribed. Do not give Aranesp to other people even if they have the same symptoms that you have. It may harm them. You can ask your healthcare provider or pharmacist for information about Aranesp that is written for healthcare professionals.

What are the ingredients in Aranesp?
Active ingredient: darbepoetin alfa
Inactive ingredients: polysorbate 80, sodium chloride, sodium phosphate dibasic anhydrous, and sodium phosphate monobasic monohydrate in Water for Injection, USP.
Manufactured by:
Amgen Inc.
One Amgen Center Drive
Thousand Oaks, CA 91320-1799 U.S.A.
U.S. License Number 1080
© 2001-2024 Amgen Inc. All rights reserved.
1xxxxxx – v10
For more information, go to the following website: www.aranesp.com or call 1-800-77-AMGEN.

This Medication Guide has been approved by the U.S. Food and Drug Administration Revised: 12/2024

Instructions for Use
ARANESP® (Air-uh-nesp)
(darbepoetin alfa)
Single-Dose Vial

Use these Instructions for Use if you or your caregiver has been trained to give Aranesp injections at home. Do not give yourself the injection unless you have received training from your healthcare provider. If you are not sure about giving the injection or if you have questions, ask your healthcare provider for help.

Before reading these Instructions for Use, read the Medication Guide that comes with Aranesp for the most important information you need to know.

When you receive your Aranesp vial and syringes make sure that:

- The name Aranesp appears on the carton and vial label.
- The expiration date on the vial label has not passed. Do not use a vial of Aranesp after the expiration date on the label.
- The dose strength of the Aranesp vial (number of micrograms [mcg] in the colored square on the package and on the vial label) is the same as your healthcare provider prescribed.
- The Aranesp liquid in the vial is clear and colorless. Do not use Aranesp if the liquid in the vial looks discolored or cloudy, or if the liquid has lumps, flakes, or particles.
- The Aranesp vial has a color cap on the top of the vial. Do not use a vial of Aranesp if the color cap on the top of the vial has been removed or is missing.
- Use only the type of disposable syringe and needle that your healthcare provider has prescribed.
- Do not shake Aranesp. Shaking could cause Aranesp not to work. If you shake Aranesp, the solution in the vial may look foamy and should not be used.
- Do not freeze Aranesp. Do not use a vial of Aranesp that has been frozen.
- Store Aranesp in the refrigerator between 36°F to 46°F (2°C to 8°C).
- Keep Aranesp away from light.
- Single-dose vials of Aranesp should be used only one time. Throw the vial away after use even if there is medicine left in the vial.

How should I prepare for an injection of Aranesp?

- Always keep an extra syringe and needle on hand.
- Follow your healthcare provider’s instructions on how to measure your dose of Aranesp. This dose will be measured in milliliter (mL) or cc (1 mL is the same as 1 cc). Use a syringe that is marked in tenths of mL (for example, 0.2 mL or 0.2 cc). Using the wrong syringe can lead to a mistake in your dose and you could inject too much or too little Aranesp.

Only use disposable syringes and needles. Use the syringes and needles only one time and then throw them away as instructed by your healthcare provider.

Important: Follow these instructions exactly to help avoid infections.

Preparing the dose:

1. Remove the vial of Aranesp from the refrigerator. During this time, protect the solution from light. Keep the vial in its carton until you are ready to prepare the dose. Do not leave the vial in light.

2. Do not use a single-dose vial of Aranesp more than one time.

3. Do not shake Aranesp.

4. Gather the other supplies you will need for your injection (vial, syringe, alcohol wipes, cotton ball, and a puncture-proof container for throwing away the syringe and needle). See Figure 1.

5. Check the date on the Aranesp vial to be sure that the drug has not expired.

6. Wash your hands well with soap and water before preparing the medicine. See Figure 2.

7. Flip off the protective color cap on the top of the vial. Do not remove the grey rubber stopper. Wipe the top of the grey rubber stopper with an alcohol wipe. See Figures 3 and 4.

8. Check the package containing the syringe. If the package has been opened or damaged, do not use that syringe. Throw away the syringe in the puncture-proof disposable container. If the syringe package is undamaged, open the package and remove the syringe.

9. Using a syringe and needle that has been recommended by your healthcare provider, carefully remove the needle cover. See Figure 5. Then draw air into the syringe by pulling back on the plunger. The amount of air drawn into the syringe should be equal to the amount (mL or cc) of the Aranesp dose prescribed by your healthcare provider. See Figure 6.

10. With the vial on a flat work surface, insert the needle straight down through the grey rubber stopper of the Aranesp vial. See Figure 7.

11. Push the plunger of the syringe down to inject the air from the syringe into the vial of Aranesp. The air injected into the vial will allow Aranesp to be easily withdrawn into the syringe. See Figure 7.

12. Keep the needle inside the vial. Turn the vial and syringe upside down. Be sure the tip of the needle is in the Aranesp liquid. Keep the vial upside down. Slowly pull back on the plunger to fill the syringe with Aranesp liquid to the number (mL or cc) that matches the dose your healthcare provider prescribed. See Figure 8.

13. Keep the needle in the vial. Check for air bubbles in the syringe. A small amount of air is harmless. Too large an air bubble will give you the wrong Aranesp dose. To remove air bubbles, gently tap the syringe with your fingers until the air bubbles rise to the top of the syringe. Slowly push the plunger up to force the air bubbles out of the syringe. Keep the tip of the needle in the Aranesp liquid. Pull the plunger back to the number on the syringe that matches your dose. Check again for air bubbles. If there are still air bubbles, repeat the steps above to remove them. See Figures 9 and 10.

14. Double-check that you have the correct dose in the syringe. Lay the vial down on its side with the needle still in it until after you have selected and prepared a site for injection.

Selecting and preparing the injection site:

Aranesp can be injected into your body using two different ways (routes) as described below. Follow your healthcare provider’s instructions about how you should inject Aranesp. For patients on hemodialysis, the intravenous (IV) route is recommended.

1. Subcutaneous Route:

- Aranesp can be injected directly into a layer of fat under your skin. This is called a subcutaneous injection. When giving subcutaneous injections, follow your healthcare provider’s instructions about changing the site for each injection. You may wish to write down the site where you have injected.
- Do not inject Aranesp into an area that is tender, red, bruised, hard, or has scars or stretch marks. Recommended sites for injection are shown in Figure 11 below, including:
  ° The outer area of the upper arms
  ° The abdomen (except for the 2-inch area around the navel)
  ° The front of the middle thighs
  ° The upper outer area of the buttocks

- Clean the skin with an alcohol wipe where the injection is to be made. Be careful not to touch the skin that has been wiped clean. See Figure 12.

- Double-check that the correct amount of Aranesp is in the syringe.
- Remove the prepared syringe and needle from the vial of Aranesp and hold it in the hand that you will use to inject the medicine.
- Use the other hand to pinch a fold of skin at the cleaned injection site. Do not touch the cleaned area of skin. See Figure 13.

- Hold the syringe like you would hold a pencil. Use a quick “dart-like” motion to insert the needle either straight up and down (90-degree angle) or at a slight angle (45 degrees) into the skin. Inject the prescribed dose subcutaneously as directed by your doctor, nurse, or pharmacist. See Figure 14.

- Pull the needle out of the skin and press a cotton ball or gauze over the injection site and hold it there for several seconds. Do not recap the needle.
- Dispose of the used syringe and needle as described below. Do not reuse syringes and needles.

2. Intravenous Route:

- Aranesp can be injected in your vein through a special access port placed by your healthcare provider. This type of Aranesp injection is called an intravenous (IV) injection. This route is usually for hemodialysis patients.
- If you have a dialysis vascular access, make sure it is working by checking it as your healthcare provider has shown you. Be sure to let your healthcare provider know right away if you are having any problems, or if you have any questions.
- Wipe off the venous port of the hemodialysis tubing with an alcohol wipe. See Figure 15.

- Insert the needle of the syringe into the cleaned venous port and push the plunger all the way down to inject all the Aranesp. See Figure 16.

- Remove the syringe from the venous port. Do not recap the needle.
- Dispose of the used syringe and needle as described below.

How should I dispose of the vials, syringes, and needles?

Do not reuse the single-dose vials, syringes, or needles. Throw away the vials, syringes, and needles as instructed by your healthcare provider or by following these steps:

- Do not throw the vials, syringes, or needles in the household trash or recycle.
- Do not put the needle cover back on the needle.
- Place all used needles and syringes in a puncture-proof disposable container with a lid. Do not use glass or clear plastic containers, or any container that will be recycled or returned to a store.
- Keep the puncture-proof disposable container out of the reach of children.
- When the puncture-proof disposable container is full, tape around the cap or lid to make sure the cap or lid does not come off. Throw away the puncture-proof disposable container as instructed by your healthcare provider. There may be special state and local laws for disposing of used needles and syringes. Do not throw the puncture-proof disposable container in the household trash. Do not recycle.

Keep Aranesp and all medicines out of the reach of children.

These Instructions for Use have been approved by the U.S. Food and Drug Administration.

Manufactured by:

Amgen Inc.
One Amgen Center Drive
Thousand Oaks, CA 91320-1799 U.S.A.

Revised: 12/2024

© 2001-2012, 2024 Amgen Inc. All rights reserved.

1xxxxxx – v4

Instructions for Use
ARANESP® (Air-uh-nesp)
(darbepoetin alfa)
Injection
Single-Dose Prefilled Syringe (SingleJect®)

Guide to parts

Important: The needle is covered by the needle cap before use.

Important

Read the Medication Guide for important information you need to know about Aranesp before using these Instructions for Use.

Before you use an Aranesp prefilled syringe, read this important information

Storing your prefilled syringe

- Keep the prefilled syringe in the original carton to protect from light or physical damage.
- Store the prefilled syringe in the refrigerator between 36° F to 46° F (2° C to 8° C).
- Do not use a prefilled syringe that has been frozen.
- After you inject your dose, throw away (dispose of) any unused Aranesp left in the prefilled syringe. Do not save unused Aranesp in the prefilled syringe for later use.
- Keep the Aranesp prefilled syringe out of the reach of children.

Using your prefilled syringe

- It is important that you do not try to give the injection unless you or your caregiver has received training from your healthcare provider.
- Make sure the name Aranesp appears on the carton and prefilled syringe label.
- Do not use a prefilled syringe after the expiration date on the label.
- Do not use a prefilled syringe that has been shaken.
- Do not remove the gray needle cap from the prefilled syringe until you are ready to inject.
- Do not use the prefilled syringe if the pack is open or damaged.
- Do not use a prefilled syringe if it has been dropped on a hard surface. The prefilled syringe may be broken even if you cannot see the break. Use a new prefilled syringe.
- Do not slide the yellow safety guard over the needle before you give the injection. This will “activate” or lock the yellow safety guard. Use another prefilled syringe that has not been activated and is ready to use.
- The gray needle cap on the prefilled syringe contains dry natural rubber (made from latex). Tell your healthcare provider if you are allergic to latex.

Call your healthcare provider if you have any questions.

Step 1: Prepare

A Remove one prefilled syringe from the refrigerator.

The original pack with any unused prefilled syringes should remain in the refrigerator.

- Do not use the prefilled syringe if the pack is damaged.
- Do not try to warm the prefilled syringe by using a heat source such as hot water or microwave.
- Do not leave the prefilled syringe in direct sunlight.
- Do not shake the prefilled syringe.

Open the package and remove the syringe from the tray. Grab the yellow safety guard to remove the prefilled syringe from the tray.

For safety reasons:

- Do not grab the plunger rod.
- Do not grab the gray needle cap.

B Inspect the medicine and prefilled syringe.

Turn the prefilled syringe so you can see the medicine window and markings. Make sure the medicine in the prefilled syringe is clear and colorless.

- Do not use the prefilled syringe if:
  ° The medicine is cloudy or discolored or contains flakes or particles.
  ° Any part appears cracked or broken.
  ° The prefilled syringe has been dropped.
  ° The gray needle cap is missing or not securely attached.
  ° The expiration date printed on the label has passed.

In all cases, use a new prefilled syringe and call your healthcare provider.

C Gather all materials needed for your injection.

Wash your hands thoroughly with soap and water.

On a clean, well-lit work surface, place the:

- Prefilled syringe
- Alcohol wipe
- Cotton ball or gauze pad
- Adhesive bandage
- Sharps disposal container

Step 2: Get ready

D Prepare and clean your injection site(s).

You can use:

- Thigh
- Stomach area (abdomen), except for a 2-inch area right around your navel (belly button)
- Upper outer area of your buttocks (only if someone else is giving you the injection)
- Outer area of upper arm (only if someone else is giving you the injection)

Clean your injection site with an alcohol wipe. Let your skin dry.

- Do not touch this area again before injecting.
- If you want to use the same injection site, make sure it is not the same spot on the injection site area you used for a previous injection.
- Do not inject into areas where the skin is tender, bruised, red, or hard. Avoid injecting into areas with scars or stretch marks.

Important: Follow your healthcare provider’s instructions about selecting sites for injection appropriate to you and about changing the site for each injection.

E Hold the prefilled syringe by the syringe barrel. Carefully pull the gray needle cap straight off and away from your body.

- Do not remove the gray needle cap from the prefilled syringe until you are ready to inject.
- Do not twist or bend the gray needle cap.
- Do not hold the prefilled syringe by the plunger rod.
- Do not put the gray needle cap back onto the prefilled syringe.

Important: Throw the gray needle cap into the sharps disposal container.

Your healthcare provider has prescribed either a “full” syringe dose or a “partial” syringe dose of Aranesp.

- If you are prescribed a full dose of Aranesp, you will inject all of the medicine from your prefilled syringe. For a full dose, go directly to Step 3, and choose between the Subcutaneous or Port injection based on your healthcare provider’s instructions.
- If you are prescribed a partial dose of Aranesp, start with Step G below.

G Point the needle up and tap gently until the air rises to the top.

H Slowly push the plunger rod up to the line on the syringe barrel that matches your prescribed dose.

Important: Do not slide the yellow safety guard over the needle before you give the injection. This will “activate” or lock the yellow safety guard.

As you push the plunger rod up, air and extra medication is removed. Check to make sure the plunger lines up with the syringe marking for your prescribed dose. If you remove too much medicine, get a new prefilled syringe and start again at Step 1.

Call your healthcare provider if you have problems measuring your prescribed dose.

Step 3: Subcutaneous (under the skin) injection

I Pinch your injection site to create a firm surface.

Important: Keep skin pinched while injecting.

J Hold the pinch. Insert the needle into the skin at 45 to 90 degrees.

K Using slow and constant pressure, push the plunger rod until it reaches the bottom.

- Do not pull back the plunger rod while the needle is inserted.

When done, gently pull the syringe off of your skin, and continue to Step 4: Finish.

Important: When you remove the syringe, if it looks like the medicine is still in the syringe barrel, this means you have not received a full dose. Call your healthcare provider right away.

Step 3: Port Injection

If your healthcare provider has prescribed injection into your home hemodialysis system, you should be first trained by your healthcare provider and then follow the procedure described below.

A. Locate the port on the hemodialysis tubing where your healthcare professional prescribed you to inject. Do not inject into the hemodialysis tubing.

B. Clean the port with an alcohol wipe.

C. Insert the prefilled syringe needle at a 90° angle, directly into the center of the rubber septum located on the cleaned port. Do not bend the needle. The rubber septum may require increased pressure to penetrate with the needle.

D. Push the plunger down until it reaches the bottom.

E. Remove the prefilled syringe from the port.

Now, continue to Step 4: Finish.

Step 4: Finish

For your safety, pull the yellow safety guard until it clicks and covers the needle.

Once extended, the yellow safety guard will lock into position and will not slide back over the needle.

Keep your hands away from the needle at all times.

M Discard (throw away) the used prefilled syringe.

- Put the used syringe in a FDA-cleared sharps disposal container right away after use. Do not throw away (dispose of) the prefilled syringe in your household trash.
- If you do not have a FDA-cleared sharps disposal container, you may use a household container that is:
  ° made of a heavy-duty plastic,
  ° can be closed with a tight-fitting, puncture-resistant lid, without sharps being able to come out,
  ° upright and stable during use,
  ° leak-resistant, and
  ° properly labeled to warn of hazardous waste inside the container.
- When your sharps disposal container is almost full, you will need to follow your community guidelines for the right way to dispose of your sharps disposal container. There may be state or local laws about how you should throw away used needles and syringes. For more information about safe sharps disposal, and for specific information about sharps disposal in the state that you live in, go to the FDA’s website at: http://www.fda.gov/safesharpsdisposal
- Do not reuse the prefilled syringe.
- Do not recycle the syringe or sharps disposal container or throw them into household trash.

Important: Always keep the sharps disposal container out of the reach of children.

N Examine the injection site.

If there is blood, press a cotton ball or gauze pad on your injection site. Do not rub the injection site. Apply an adhesive bandage if needed.

This Instructions for Use has been approved by the U.S. Food and Drug Administration.

Manufactured by:

Amgen Inc.
One Amgen Center Drive
Thousand Oaks, California 91320-1799
U.S. License Number 1080
© 2001-2016, 2024 Amgen Inc. All rights reserved.
1xxxxxx
Revised: 12/2024 v5

PACKAGE LABEL - PRINCIPAL DISPLAY PANEL - PREFILLED SYRINGE, 10 MCG

NDC 55513-098-04

Single-Dose Prefilled Syringes with 27 Gauge Needles

4 x 10 mcg/0.4 mL Prefilled Syringes

AMGEN ®

Aranesp ® SingleJect ®

(darbepoetin alfa)

recombinant

Albumin Free

10 mcg

10 mcg/0.4 mL

For Intravenous or Subcutaneous Use Only

Sterile Solution – No Preservative

Store at 2° to 8°C (36° to 46°F).

Do Not Freeze or Shake. Protect from Light.

This Product Contains Dry Natural Rubber.

Rx Only

U.S. License No. 1080

©2014, 2016 Amgen Inc.

Manufactured by Amgen Inc. Thousand Oaks, CA 91320-1799 U.S.A.

PACKAGE LABEL - PRINCIPAL DISPLAY PANEL - PREFILLED SYRINGE, 25 MCG

NDC 55513-057-04

Single-Dose Prefilled Syringes with 27 Gauge Needles

4 x 25 mcg/0.42 mL Prefilled Syringes

AMGEN ®

Aranesp ® SingleJect ®

(darbepoetin alfa)

recombinant

Albumin Free

25 mcg

25 mcg/0.42 mL

For Intravenous or Subcutaneous Use Only

Sterile Solution – No Preservative

Store at 2° to 8°C (36° to 46°F).

Do Not Freeze or Shake. Protect from Light.

This Product Contains Dry Natural Rubber.

Rx Only

U.S. License No. 1080

©2012, 2016 Amgen Inc.

Manufactured by Amgen Inc. Thousand Oaks, CA 91320-1799 U.S.A.

PACKAGE LABEL - PRINCIPAL DISPLAY PANEL - PREFILLED SYRINGE, 40 MCG

NDC 55513-021-04

Single-Dose Prefilled Syringes with 27 Gauge Needles

4 x 40 mcg/0.4 mL Prefilled Syringes

AMGEN ®

Aranesp ® SingleJect ®

(darbepoetin alfa)

recombinant

Albumin Free

40 mcg

40 mcg/0.4 mL

For Intravenous or Subcutaneous Use Only

Sterile Solution – No Preservative

Store at 2° to 8°C (36° to 46°F).

Do Not Freeze or Shake. Protect from Light.

This Product Contains Dry Natural Rubber.

Rx Only

U.S. License No. 1080

©2012, 2016 Amgen Inc.

Manufactured by Amgen Inc. Thousand Oaks, CA 91320-1799 U.S.A.

PACKAGE LABEL - PRINCIPAL DISPLAY PANEL - PREFILLED SYRINGE, 60 MCG

NDC 55513-023-04

Single-Dose Prefilled Syringes with 27 Gauge Needles

4 x 60 mcg/0.3 mL Prefilled Syringes

AMGEN ®

Aranesp ® SingleJect ®

(darbepoetin alfa)

recombinant

Albumin Free

60 mcg

60 mcg/0.3 mL

For Intravenous or Subcutaneous Use Only

Sterile Solution – No Preservative

Store at 2° to 8°C (36° to 46°F).

Do Not Freeze or Shake. Protect from Light.

This Product Contains Dry Natural Rubber.

Rx Only

U.S. License No. 1080

©2012, 2016 Amgen Inc.

Manufactured by Amgen Inc. Thousand Oaks, CA 91320-1799 U.S.A.

PACKAGE LABEL - PRINCIPAL DISPLAY PANEL - PREFILLED SYRINGE, 100 MCG

NDC 55513-025-04

Single-Dose Prefilled Syringes with 27 Gauge Needles

4 x 100 mcg/0.5 mL Prefilled Syringes

AMGEN ®

Aranesp ® SingleJect ®

(darbepoetin alfa)

recombinant

Albumin Free

100 mcg

100 mcg/0.5 mL

For Intravenous or Subcutaneous Use Only

Sterile Solution – No Preservative

Store at 2° to 8°C (36° to 46°F).

Do Not Freeze or Shake. Protect from Light.

This Product Contains Dry Natural Rubber.

Rx Only

U.S. License No. 1080

©2012, 2016 Amgen Inc.

Manufactured by Amgen Inc. Thousand Oaks, CA 91320-1799 U.S.A.

PACKAGE LABEL - PRINCIPAL DISPLAY PANEL - PREFILLED SYRINGE, 150 MCG

NDC 55513-027-04

Single-Dose Prefilled Syringes with 27 Gauge Needles

4 x 150 mcg/0.3 mL Prefilled Syringes

AMGEN ®

Aranesp ® SingleJect ®

(darbepoetin alfa)

recombinant

Albumin Free

150 mcg

150 mcg/0.3 mL

For Intravenous or Subcutaneous Use Only

Sterile Solution – No Preservative

Store at 2° to 8°C (36° to 46°F).

Do Not Freeze or Shake. Protect from Light.

This Product Contains Dry Natural Rubber.

Rx Only

U.S. License No. 1080

©2012, 2016 Amgen Inc.

Manufactured by Amgen Inc. Thousand Oaks, CA 91320-1799 U.S.A.

PACKAGE LABEL - PRINCIPAL DISPLAY PANEL - PREFILLED SYRINGE, 200 MCG

NDC 55513-028-01

Single-Dose Prefilled Syringe with 27 Gauge Needle

1 x 200 mcg/0.4 mL Prefilled Syringe

AMGEN ®

Aranesp ® SingleJect ®

(darbepoetin alfa)

recombinant

Albumin Free

200 mcg

200 mcg/0.4 mL

ATTENTION: Enclosed medication guide is required for each patient.
For more copies see aranesp.com or call 1-800-77AMGEN.

Store at 2° to 8°C (36° to 46°F).

Do Not Freeze or Shake. Protect from Light.

This Product Contains Dry Natural Rubber.

Rx Only

Manufactured by Amgen Inc. Thousand Oaks, CA 91320-1799 U.S.A.

PACKAGE LABEL - PRINCIPAL DISPLAY PANEL - PREFILLED SYRINGE, 300 MCG

NDC 55513-111-01

Single-Dose Prefilled Syringe with 27 Gauge Needle

1 x 300 mcg/0.6 mL Prefilled Syringe

AMGEN ®

Aranesp ® SingleJect ®

(darbepoetin alfa)

recombinant

Albumin Free

300 mcg

300 mcg/0.6 mL

ATTENTION: Enclosed medication guide is required for each patient.
For more copies see aranesp.com or call 1-800-77AMGEN.

Store at 2° to 8°C (36° to 46°F).

Do Not Freeze or Shake. Protect from Light.

This Product Contains Dry Natural Rubber.

Rx Only

Manufactured by Amgen Inc. Thousand Oaks, CA 91320-1799 U.S.A.

PACKAGE LABEL - PRINCIPAL DISPLAY PANEL - PREFILLED SYRINGE, 500 MCG

NDC 55513-032-01

Single-Dose Prefilled Syringe with 27 Gauge Needle

1 x 500 mcg/1 mL Prefilled Syringe

AMGEN ®

Aranesp ® SingleJect ®

(darbepoetin alfa)

recombinant

Albumin Free

500 mcg

500 mcg/1 mL

ATTENTION: Enclosed medication guide is required for each patient.
For more copies see aranesp.com or call 1-800-77AMGEN.

Store at 2° to 8°C (36° to 46°F).

Do Not Freeze or Shake. Protect from Light.

This Product Contains Dry Natural Rubber.

Rx Only

Manufactured by Amgen Inc. Thousand Oaks, CA 91320-1799 U.S.A.

PACKAGE LABEL - PRINCIPAL DISPLAY PANEL - VIAL, 25 MCG

NDC 55513-002-04

Single-Dose Vials

4 x 25 mcg/1 mL Single-Dose Vials

AMGEN ®

Aranesp ®

(darbepoetin alfa)

recombinant

Albumin Free

25 mcg

25 mcg/1 mL

For Intravenous or Subcutaneous Use Only

Sterile Solution – No Preservative

Store at 2° to 8°C (36° to 46°F). Do Not Freeze or Shake.

Protect from Light.

Rx Only

U.S. License No. 1080

©2012, 2016 Amgen Inc.

Manufactured by Amgen Inc.

Thousand Oaks, CA 91320-1799 U.S.A.

PACKAGE LABEL - PRINCIPAL DISPLAY PANEL - VIAL, 40 MCG

NDC 55513-003-04

Single-Dose Vials

4 x 40 mcg/1 mL Single-Dose Vials

AMGEN ®

Aranesp ®

(darbepoetin alfa)

recombinant

Albumin Free

40 mcg

40 mcg/1 mL

For Intravenous or Subcutaneous Use Only

Sterile Solution – No Preservative

Store at 2° to 8°C (36° to 46°F). Do Not Freeze or Shake.

Protect from Light.

Rx Only

U.S. License No. 1080

©2012, 2016 Amgen Inc.

Manufactured by Amgen Inc.

Thousand Oaks, CA 91320-1799 U.S.A.

PACKAGE LABEL - PRINCIPAL DISPLAY PANEL - VIAL, 60 MCG

NDC 55513-004-04

Single-Dose Vials

4 x 60 mcg/1 mL Single-Dose Vials

AMGEN ®

Aranesp ®

(darbepoetin alfa)

recombinant

Albumin Free

60 mcg

60 mcg/1 mL

For Intravenous or Subcutaneous Use Only

Sterile Solution – No Preservative

Store at 2° to 8°C (36° to 46°F). Do Not Freeze or Shake.

Protect from Light.

Rx Only

U.S. License No. 1080

©2012, 2016 Amgen Inc.

Manufactured by Amgen Inc.

Thousand Oaks, CA 91320-1799 U.S.A.

PACKAGE LABEL - PRINCIPAL DISPLAY PANEL - VIAL, 100 MCG

NDC 55513-005-04

Single-Dose Vials

4 x 100 mcg/1 mL Single-Dose Vials

AMGEN ®

Aranesp ®

(darbepoetin alfa)

recombinant

Albumin Free

100 mcg

100 mcg/1 mL

For Intravenous or Subcutaneous Use Only

Sterile Solution – No Preservative

Store at 2° to 8°C (36° to 46°F). Do Not Freeze or Shake.

Protect from Light.

Rx Only

U.S. License No. 1080

©2012, 2016 Amgen Inc.

Manufactured by Amgen Inc.

Thousand Oaks, CA 91320-1799 U.S.A.

PACKAGE LABEL - PRINCIPAL DISPLAY PANEL - VIAL, 200 MCG

NDC 55513-006-01

1 x 200 mcg/1 mL Single-Dose Vial

AMGEN ®

Aranesp ®

(darbepoetin alfa)

recombinant

Albumin Free

200 mcg

200 mcg/1 mL

Store at 2° to 8°C (36° to 46°F).

Do Not Freeze or Shake.

Protect from Light.

For IV or SC Use Only

Sterile Solution – No Preservative

Rx Only

Manufactured by Amgen Inc.

Thousand Oaks, CA 91320-1799 U.S.A.